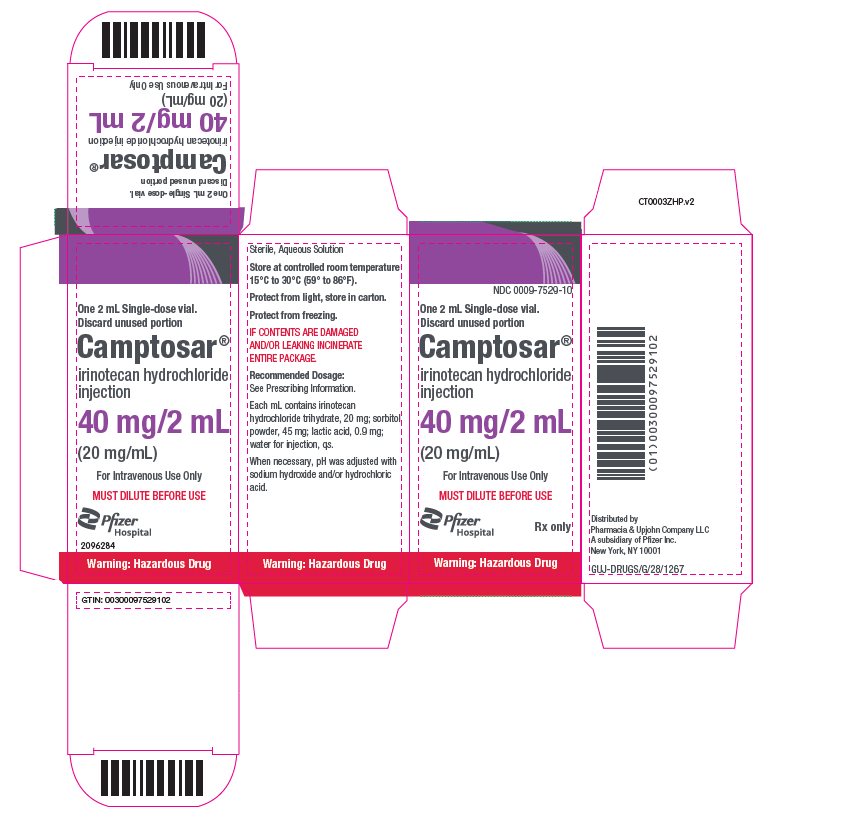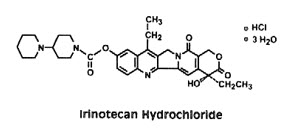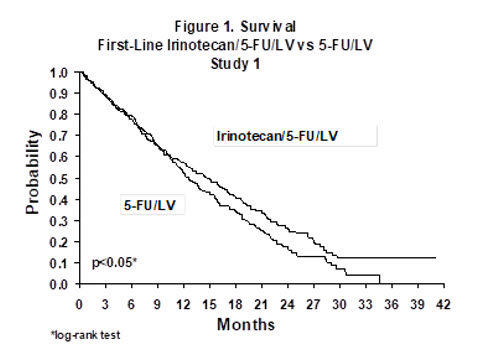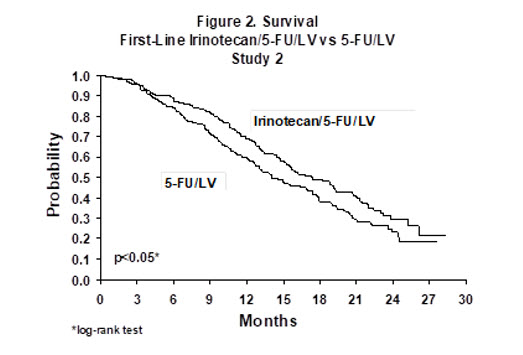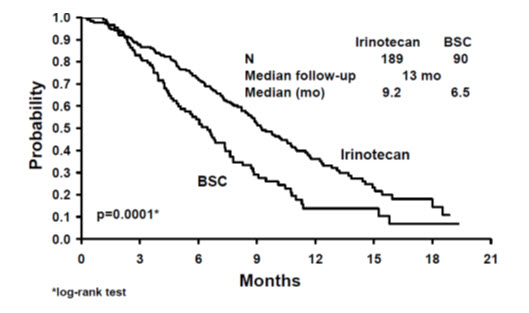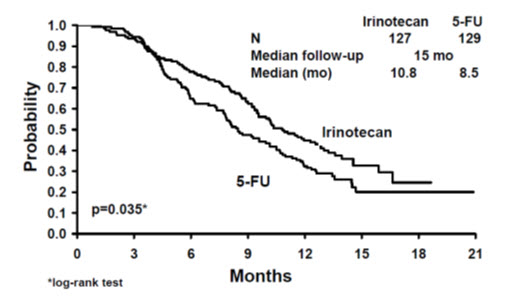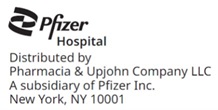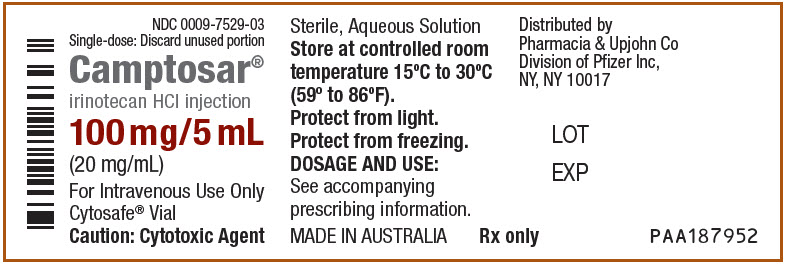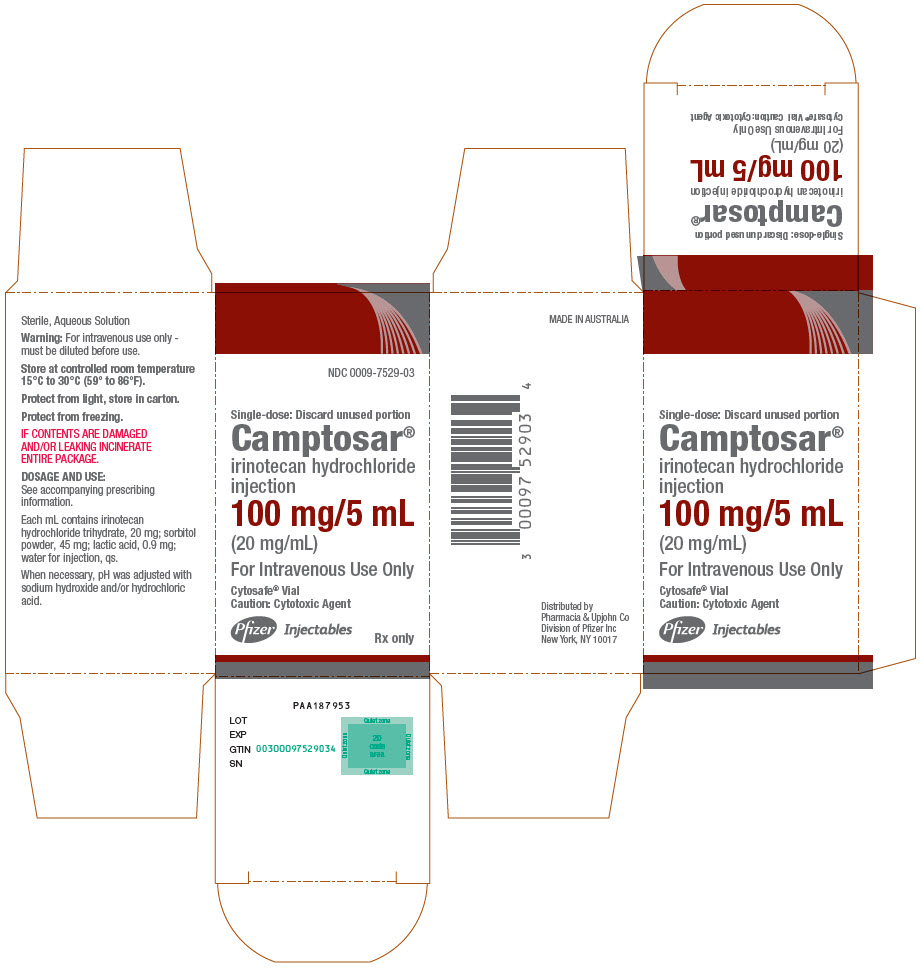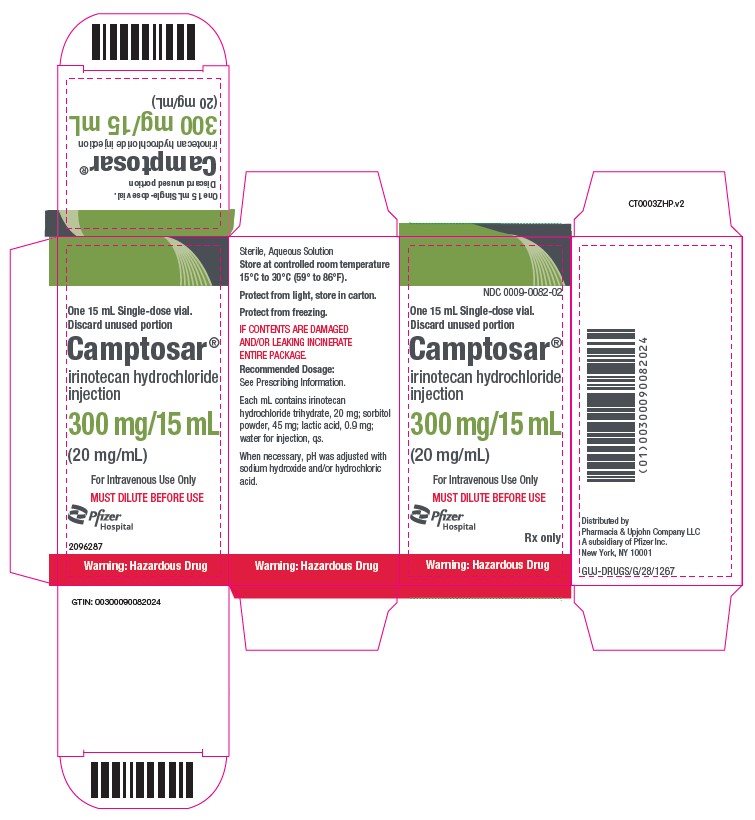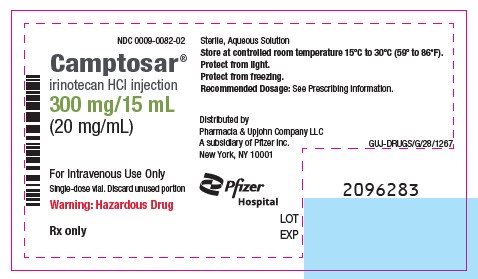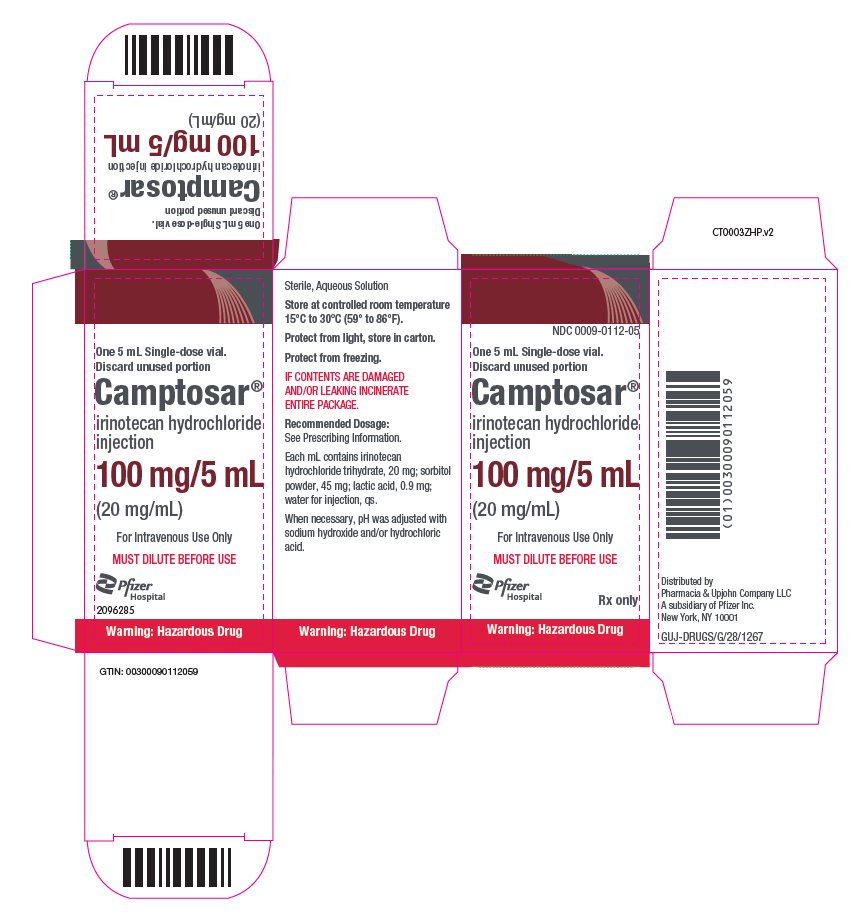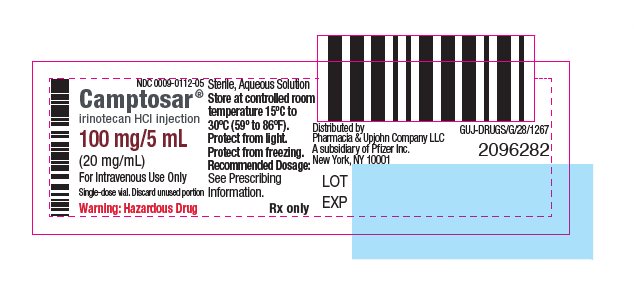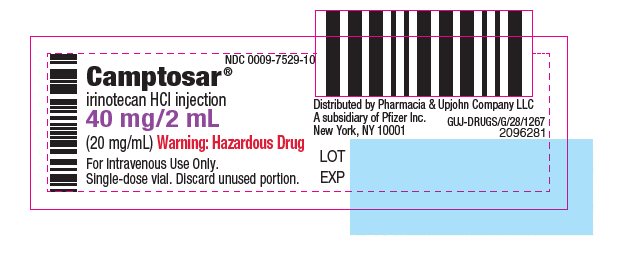 DRUG LABEL: Camptosar
NDC: 0009-7529 | Form: INJECTION, SOLUTION
Manufacturer: Pharmacia & Upjohn Company LLC
Category: prescription | Type: HUMAN PRESCRIPTION DRUG LABEL
Date: 20250930

ACTIVE INGREDIENTS: IRINOTECAN HYDROCHLORIDE 20 mg/1 mL
INACTIVE INGREDIENTS: LACTIC ACID, UNSPECIFIED FORM; SODIUM HYDROXIDE; HYDROCHLORIC ACID

HIGHLIGHTS OF PRESCRIBING INFORMATION

These highlights do not include all the information needed to use CAMPTOSAR safely and effectively. See full prescribing information for CAMPTOSAR.
CAMPTOSAR® (irinotecan hydrochloride) injection, for intravenous use
Initial U.S. Approval: 1996

WARNING: DIARRHEA and MYELOSUPPRESSION

See full prescribing information for complete boxed warning.

- Early and late forms of diarrhea can occur. Early diarrhea may be accompanied by cholinergic symptoms which may be prevented or ameliorated by atropine. Late diarrhea can be life threatening and should be treated promptly with loperamide. Monitor patients with diarrhea and give fluid and electrolytes as needed. Institute antibiotic therapy if patients develop ileus, fever, or severe neutropenia. Interrupt CAMPTOSAR and reduce subsequent doses if severe diarrhea occurs. (2.2, 5.1)
- Severe myelosuppression may occur. (5.2)

1 INDICATIONS AND USAGE

CAMPTOSAR is a topoisomerase inhibitor indicated for:

- First-line therapy in combination with 5-fluorouracil and leucovorin for patients with metastatic carcinoma of the colon or rectum. (1)
- Patients with metastatic carcinoma of the colon or rectum whose disease has recurred or progressed following initial fluorouracil-based therapy. (1)

2 DOSAGE AND ADMINISTRATION

- Colorectal cancer combination regimen 1: CAMPTOSAR 125 mg/m^2 intravenous infusion over 90 minutes on days 1, 8,15, 22 with LV 20 mg/m^2 intravenous bolus infusion on days 1, 8, 15, 22 followed by 5-FU intravenous bolus infusion on days 1, 8, 15, 22 every 6 weeks. (2.1)
- Colorectal cancer combination regimen 2: CAMPTOSAR 180 mg/m^2 intravenous infusion over 90 minutes on days 1, 15, 29 with LV 200 mg/m^2 intravenous infusion over 2 hours on days 1, 2, 15, 16, 29, 30 followed by 5-FU 400 mg/m^2 intravenous bolus infusion on days 1, 2, 15, 16, 29, 30 and 5-FU 600 mg/m^2 intravenous infusion over 22 hours on days 1, 2, 15, 16, 29, 30. (2.1)
- Colorectal cancer single agent regimen 1: CAMPTOSAR 125 mg/m^2 intravenous infusion over 90 minutes on days 1, 8, 15, 22 then 2-week rest. (2.2)
- Colorectal cancer single agent regimen 2: CAMPTOSAR 350 mg/m^2 intravenous infusion over 90 minutes on day 1 every 3 weeks. (2.2)

3 DOSAGE FORMS AND STRENGTHS

Injection: 40 mg/2 mL (20 mg/mL), 100 mg/5 mL (20 mg/mL), and 300 mg/15 mL (20 mg/mL) solution in a single-dose vial. (3)

4 CONTRAINDICATIONS

- Hypersensitivity to CAMPTOSAR or its excipients (4)

5 WARNINGS AND PRECAUTIONS

- Diarrhea and Cholinergic Reactions: Early diarrhea (occurring during or shortly after infusion of CAMPTOSAR) is usually transient and may be accompanied by cholinergic symptoms. Consider prophylactic or therapeutic administration of 0.25 mg to 1 mg of intravenous or subcutaneous atropine (unless clinically contraindicated). Late diarrhea (generally occurring more than 24 hours after administration of CAMPTOSAR) can occur. Monitor and replace fluid and electrolytes. Treat with loperamide. Use antibiotic support for ileus and fever. Interrupt CAMPTOSAR and reduce subsequent doses if severe diarrhea occurs. (5.1)
- Myelosuppression: Manage promptly with antibiotic support. Interrupt CAMPTOSAR and reduce subsequent doses if necessary. (5.2)
- Increased Risk of Neutropenia in Patients With Reduced UGT1A1 Activity: Individuals with UGT1A1*28/*28, or *6/*6, or *6/*28 genotypes are at increased risk for severe neutropenia during CAMPTOSAR treatment. (5.3)
- Hypersensitivity: Hypersensitivity reactions including severe anaphylactic or anaphylactoid reactions have been observed. Discontinue CAMPTOSAR if this occurs. (5.4)
- Renal Impairment/Renal Failure: Rare cases of renal impairment and acute renal failure have been identified, usually in patients who became volume depleted from severe vomiting and/or diarrhea. (5.5)
- Pulmonary Toxicity: Interstitial Pulmonary Disease (IPD)-like events, including fatalities, have occurred. Interrupt for new or progressive dyspnea, cough, and fever pending evaluation. If IPD diagnosed, discontinue and institute appropriate treatment as needed. (5.6)
- Toxicity of the 5 Day Regimen: CAMPTOSAR should not be used in combination with a regimen of 5-FU/LV administered for 4–5 consecutive days every 4 weeks outside of a clinical study. (5.7)
- Embryo-Fetal Toxicity: CAMPTOSAR can cause fetal harm. Advise females of reproductive potential of the potential risk to a fetus and to use effective contraception. Advise male patients with female partners of reproductive potential to use condoms. (5.9, 8.1, 8.3)
- Patients With Hepatic Impairment: In clinical trials, CAMPTOSAR has not been administered to patients with serum bilirubin > 2.0 mg/dL, or transaminases > 3 times ULN if no liver metastases, or transaminases > 5 times ULN if liver metastases. With the weekly dosage schedule, patients with total bilirubin levels 1.0–2.0 mg/dL had greater likelihood of grade 3–4 neutropenia. (5.10)

6 ADVERSE REACTIONS

Common adverse reactions (≥30%) observed in combination therapy clinical studies are: nausea, vomiting, abdominal pain, diarrhea, constipation, anorexia, mucositis, neutropenia, leukopenia (including lymphocytopenia), anemia, thrombocytopenia, asthenia, pain, fever, infection, abnormal bilirubin, alopecia. (6.1)

Common adverse reactions (≥30%) observed in single agent therapy clinical studies are: nausea, vomiting, abdominal pain, diarrhea, constipation, anorexia, neutropenia, leukopenia (including lymphocytopenia), anemia, asthenia, fever, body weight decreasing, alopecia. (6.1)
To report SUSPECTED ADVERSE REACTIONS, contact Pfizer Inc, at 1-800-438-1985 or FDA at 1-800-FDA-1088 or www.fda.gov/medwatch.

7 DRUG INTERACTIONS

- Strong CYP3A4 Inducers: Do not administer strong CYP3A4 inducers with CAMPTOSAR. (7.2)
- Strong CYP3A4 Inhibitors: Do not administer strong CYP3A4 inhibitors with CAMPTOSAR. (7.3)

8 USE IN SPECIFIC POPULATIONS

- Lactation: Advise not to breastfeed. (8.2)
- Geriatric Use: Closely monitor patients greater than 65 years of age because of a greater risk of early and late diarrhea in this population. (8.5)
- Patients With Renal Impairment: Use caution and do not use in patients on dialysis. (8.6)
- Patients With Hepatic Impairment: Use caution. (2.1, 5.10, 8.7, 12.3)

FULL PRESCRIBING INFORMATION

WARNING: DIARRHEA and MYELOSUPPRESSION

- Early and late forms of diarrhea can occur. Early diarrhea may be accompanied by cholinergic symptoms which may be prevented or ameliorated by atropine. Late diarrhea can be life threatening and should be treated promptly with loperamide. Monitor patients with diarrhea and give fluid and electrolytes as needed. Institute antibiotic therapy if patients develop ileus, fever, or severe neutropenia. Interrupt CAMPTOSAR and reduce subsequent doses if severe diarrhea occurs [see Dosage and Administration (2.2) and Warnings and Precautions (5.1)].
- Severe myelosuppression may occur [see Warnings and Precautions (5.2)].

1 INDICATIONS AND USAGE

- CAMPTOSAR is indicated as a component of first-line therapy in combination with 5-fluorouracil (5-FU) and leucovorin (LV) for patients with metastatic carcinoma of the colon or rectum.
- CAMPTOSAR is indicated for patients with metastatic carcinoma of the colon or rectum whose disease has recurred or progressed following initial fluorouracil-based therapy.

2 DOSAGE AND ADMINISTRATION

2.1 Colorectal Cancer Combination Regimens 1 and 2

Administer CAMPTOSAR as a 90-minute intravenous infusion followed by LV and 5-FU. The currently recommended regimens are shown in Table 1.

A reduction in the starting dose by one dose level of CAMPTOSAR may be considered for patients with any of the following conditions: prior pelvic/abdominal radiotherapy, performance status of 2, or increased bilirubin levels. Dosing for patients with bilirubin >2 mg/dL cannot be recommended because there is insufficient information to recommend a dose in these patients.

Table 1. Combination-Agent Dosage Regimens and Dose Modifications [Dose reductions beyond Dose Level –2 by decrements of ≈ 20% may be warranted for patients continuing to experience toxicity. Provided intolerable toxicity does not develop, treatment with additional cycles may be continued indefinitely as long as patients continue to experience clinical benefit.]
Regimen 1 6-wk cycle with bolus 5-FU/LV (next cycle begins on day 43) | CAMPTOSAR LV 5-FU | 125 mg/m^2 intravenous infusion over 90 minutes, days 1,8,15,22 20 mg/m^2 intravenous injection bolus, days 1,8,15,22 500 mg/m^2 intravenous injection bolus, days 1,8,15,22
Regimen 1 6-wk cycle with bolus 5-FU/LV (next cycle begins on day 43) | CAMPTOSAR LV 5-FU | Starting Dose & Modified Dose Levels (mg/m^2)
Regimen 1 6-wk cycle with bolus 5-FU/LV (next cycle begins on day 43) | CAMPTOSAR LV 5-FU | Starting Dose | Dose Level -1 | Dose Level -2
 | CAMPTOSAR | 125 | 100 | 75
 | LV | 20 | 20 | 20
 | 5-FU | 500 | 400 | 300
Regimen 2 6-wk cycle with infusional 5-FU/LV (next cycle begins on day 43) | CAMPTOSAR | 180 mg/m^2 intravenous infusion over 90 minutes, days 1,15,29
Regimen 2 6-wk cycle with infusional 5-FU/LV (next cycle begins on day 43) | LV | 200 mg/m^2 intravenous infusion over 2 hours, days 1,2,15,16,29,30
Regimen 2 6-wk cycle with infusional 5-FU/LV (next cycle begins on day 43) | 5-FU Bolus | 400 mg/m^2 intravenous injection bolus, days 1,2,15,16,29,30
Regimen 2 6-wk cycle with infusional 5-FU/LV (next cycle begins on day 43) | 5-FU Infusion [Infusion follows bolus administration.] | 600 mg/m^2 intravenous infusion over 22 hours, days 1,2,15,16,29,30
 |  | Starting Dose & Modified Dose Levels (mg/m^2)
 |  | Starting Dose | Dose Level -1 | Dose Level -2
 | CAMPTOSAR | 180 | 150 | 120
 | LV | 200 | 200 | 200
 | 5-FU Bolus | 400 | 320 | 240
 | 5-FU Infusion | 600 | 480 | 360

Dosing for patients with bilirubin >2 mg/dL cannot be recommended because there is insufficient information to recommend a dose in these patients [see Warnings and Precautions (5.10), Use in Specific Populations (8.7) and Clinical Pharmacology (12.3)].

Dose Modifications

Based on recommended dose levels described in Table 1, Combination Regimens of CAMPTOSAR and Dose Modifications, subsequent doses should be adjusted as suggested in Table 2, Recommended Dose Modifications for Combination Regimens. All dose modifications should be based on the worst preceding toxicity.

Table 2. Recommended Dose Modifications for CAMPTOSAR/5-Fluorouracil (5-FU)/Leucovorin (LV) Combination Schedules
Patients should return to pre-treatment bowel function without requiring antidiarrhea medications for at least 24 hours before the next chemotherapy administration. A new cycle of therapy should not begin until the granulocyte count has recovered to ≥1500/mm^3, and the platelet count has recovered to ≥100,000/mm^3, and treatment-related diarrhea is fully resolved. Treatment should be delayed 1 to 2 weeks to allow for recovery from treatment-related toxicities. If the patient has not recovered after a 2-week delay, consideration should be given to discontinuing therapy.
Toxicity NCI CTC Grade [National Cancer Institute Common Toxicity Criteria (version 1.0)] (Value) | During a Cycle of Therapy | At the Start of Subsequent Cycles of Therapy [Relative to the starting dose used in the previous cycle]
No toxicity | Maintain dose level | Maintain dose level
Neutropenia
1 (1500 to 1999/mm^3) | Maintain dose level | Maintain dose level
2 (1000 to 1499/mm^3) | ↓ 1 dose level | Maintain dose level
3 (500 to 999/mm^3) | Omit dose until resolved to ≤ grade 2, then ↓ 1 dose level | ↓ 1 dose level
4 (<500/mm^3) | Omit dose until resolved to ≤ grade 2, then ↓ 2 dose levels | ↓ 2 dose levels
Neutropenic fever | Omit dose until resolved, then ↓ 2 dose levels
Other hematologic toxicities | Dose modifications for leukopenia or thrombocytopenia during a cycle of therapy and at the start of subsequent cycles of therapy are also based on NCI toxicity criteria and are the same as recommended for neutropenia above.
Diarrhea
1 (2–3 stools/day > pretx [Pretreatment]) | Delay dose until resolved to baseline, then give same dose | Maintain dose level
2 (4–6 stools/day > pretx) | Omit dose until resolved to baseline, then ↓ 1 dose level | Maintain dose level
3 (7–9 stools/day > pretx) | Omit dose until resolved to baseline, then ↓ 1 dose level | ↓ 1 dose level
4 (≥10 stools/day > pretx) | Omit dose until resolved to baseline, then ↓ 2 dose levels | ↓ 2 dose levels
Other nonhematologic toxicities [Excludes alopecia, anorexia, asthenia]
1 | Maintain dose level | Maintain dose level
2 | Omit dose until resolved to ≤ grade 1, then ↓ 1 dose level | Maintain dose level
3 | Omit dose until resolved to ≤ grade 2, then ↓ 1 dose level | ↓ 1 dose level
4 | Omit dose until resolved to ≤ grade 2, then ↓ 2 dose levels | ↓ 2 dose levels
 | For mucositis/stomatitis decrease only 5-FU, not CAMPTOSAR | For mucositis/stomatitis decrease only 5-FU, not CAMPTOSAR.

2.2 Colorectal Single Agent Regimens 1 and 2

Administer CAMPTOSAR as a 90-minute intravenous infusion. The currently recommended regimens are shown in Table 3.

A reduction in the starting dose by one dose level of CAMPTOSAR may be considered for patients with any of the following conditions: prior pelvic/abdominal radiotherapy, performance status of 2, or increased bilirubin levels. Dosing for patients with bilirubin >2 mg/dL cannot be recommended because there is insufficient information to recommend a dose in these patients.

Table 3. Single-Agent Regimens of CAMPTOSAR and Dose Modifications
Regimen 1 (weekly) [Subsequent doses may be adjusted as high as 150 mg/m^2 or to as low as 50 mg/m^2 in 25 to 50 mg/m^2 decrements depending upon individual patient tolerance.] | 125 mg/m^2 intravenous infusion over 90 minutes, days 1,8,15,22 then 2-week rest
 | Starting Dose and Modified Dose Levels [Provided intolerable toxicity does not develop, treatment with additional cycles may be continued indefinitely as long as patients continue to experience clinical benefit.] (mg/m^2)
 | Starting Dose | Dose Level -1 | Dose Level -2
 | 125 | 100 | 75
Regimen 2 (every 3 weeks) [Subsequent doses may be adjusted as low as 200 mg/m^2 in 50 mg/m^2 decrements depending upon individual patient tolerance.] | 350 mg/m^2 intravenous infusion over 90 minutes, once every 3 weeks
 | Starting Dose and Modified Dose Levels (mg/m^2)
 | Starting Dose | Dose Level -1 | Dose Level -2
 | 350 | 300 | 250

Dose Modifications

Based on recommended dose-levels described in Table 3, Single-Agent Regimens of CAMPTOSAR and Dose Modifications, subsequent doses should be adjusted as suggested in Table 4, Recommended Dose Modifications for Single-Agent Schedules. All dose modifications should be based on the worst preceding toxicity.

Table 4. Recommended Dose Modifications For Single-Agent Schedules [All dose modifications should be based on the worst preceding toxicity]
A new cycle of therapy should not begin until the granulocyte count has recovered to ≥1500/mm^3, and the platelet count has recovered to ≥100,000/mm^3, and treatment-related diarrhea is fully resolved. Treatment should be delayed 1 to 2 weeks to allow for recovery from treatment-related toxicities. If the patient has not recovered after a 2-week delay, consideration should be given to discontinuing CAMPTOSAR.
Worst Toxicity NCI Grade [National Cancer Institute Common Toxicity Criteria (version 1.0)] (Value) | During a Cycle of Therapy | At the Start of the Next Cycles of Therapy (After Adequate Recovery), Compared with the Starting Dose in the Previous Cycle
 | Weekly | Weekly | Once Every 3 Weeks
No toxicity | Maintain dose level | ↑ 25 mg/m^2 up to a maximum dose of 150 mg/m^2 | Maintain dose level
Neutropenia
1 (1500 to 1999/mm^3) | Maintain dose level | Maintain dose level | Maintain dose level
2 (1000 to 1499/mm^3) | ↓ 25 mg/m^2 | Maintain dose level | Maintain dose level
3 (500 to 999/mm^3) | Omit dose until resolved to ≤ grade 2, then ↓ 25 mg/m^2 | ↓ 25 mg/m^2 | ↓ 50 mg/m^2
4 (<500/mm^3) | Omit dose until resolved to ≤ grade 2, then ↓ 50 mg/m^2 | ↓ 50 mg/m^2 | ↓ 50 mg/m^2
Neutropenic fever | Omit dose until resolved, then ↓ 50 mg/m^2 when resolved | ↓ 50 mg/m^2 | ↓ 50 mg/m^2
Other hematologic toxicities | Dose modifications for leukopenia, thrombocytopenia, and anemia during a cycle of therapy and at the start of subsequent cycles of therapy are also based on NCI toxicity criteria and are the same as recommended for neutropenia above.
Diarrhea
1 (2–3 stools/day > pretx [Pretreatment]) | Maintain dose level | Maintain dose level | Maintain dose level
2 (4–6 stools/day > pretx) | ↓ 25 mg/m^2 | Maintain dose level | Maintain dose level
3 (7–9 stools/day > pretx) | Omit dose until resolved to ≤ grade 2, then ↓ 25 mg/m^2 | ↓ 25 mg/m^2 | ↓ 50 mg/m^2
4 (≥10 stools/day > pretx) | Omit dose until resolved to ≤ grade 2 then ↓ 50 mg/m^2 | ↓ 50 mg/m^2 | ↓ 50 mg/m^2
Other nonhematologic [Excludes alopecia, anorexia, asthenia] toxicities
1 | Maintain dose level | Maintain dose level | Maintain dose level
2 | ↓ 25 mg/m^2 | ↓ 25 mg/m^2 | ↓ 50 mg/m^2
3 | Omit dose until resolved to ≤ grade 2, then ↓ 25 mg/m^2 | ↓ 25 mg/m^2 | ↓ 50 mg/m^2
4 | Omit dose until resolved to ≤ grade 2, then ↓ 50 mg/m^2 | ↓ 50 mg/m^2 | ↓ 50 mg/m^2

2.3 Dosage in Patients With Reduced UGT1A1 Activity

When administered in combination with other agents, or as a single-agent, consider a reduction in the starting dose by at least one level of CAMPTOSAR for patients known to be homozygous for the UGT1A1*28 or *6 alleles (*28/*28, *6/*6) or compound heterozygous for the UGT1A1*28 and *6 alleles (*6/*28) [see Dosage and Administration (2.1, 2.2), Warnings and Precautions (5.3), and Clinical Pharmacology (12.3, 12.5)]. Subsequent dosage modifications may be required based on individual patient tolerance to treatment [see Dosage and Administration (2.1, 2.2)].

2.4 Premedication

It is recommended that patients receive premedication with antiemetic agents. In clinical studies of the weekly dosage schedule, the majority of patients received 10 mg of dexamethasone given in conjunction with another type of antiemetic agent, such as a 5-HT^3 blocker (e.g., ondansetron or granisetron). Antiemetic agents should be given on the day of treatment, starting at least 30 minutes before administration of CAMPTOSAR. Physicians should also consider providing patients with an antiemetic regimen (e.g., prochlorperazine) for subsequent use as needed. A similar antiemetic regimen should be used with CAMPTOSAR in combination therapy.

Prophylactic or therapeutic administration of atropine should be considered in patients experiencing cholinergic symptoms.

2.5 Preparation of Infusion Solution

Inspect vial contents for particulate matter and discoloration and repeat inspection when drug product is withdrawn from vial into syringe.

CAMPTOSAR Injection 20 mg/mL is intended for single use only and any unused portion should be discarded.

CAMPTOSAR Injection must be diluted prior to infusion using aseptic technique. CAMPTOSAR should be diluted in 5% Dextrose Injection, USP, (preferred) or 0.9% Sodium Chloride Injection, USP, to a final concentration range of 0.12 mg/mL to 2.8 mg/mL. Other drugs should not be added to the infusion solution.

Prepare the infusion solution immediately prior to use and commence infusion as soon as possible after preparation. If visible particulates are present in the infusion solution discard. If it is not possible to use the infusion solution immediately, the infusion solution may be stored for up to 24 hours at 2 °C to 8 °C or discarded.

2.6 Safe Handling

CAMPTOSAR is a hazardous drug. Follow applicable special handling and disposal procedures.1

Care should be exercised in the handling and preparation of infusion solutions prepared from CAMPTOSAR Injection. The use of gloves is recommended. If a solution of CAMPTOSAR contacts the skin, wash the skin immediately and thoroughly with soap and water. If CAMPTOSAR contacts the mucous membranes, flush thoroughly with water.

2.7 Extravasation

Care should be taken to avoid extravasation, and the infusion site should be monitored for signs of inflammation. Should extravasation occur, flushing the site with sterile water and applications of ice are recommended.

3 DOSAGE FORMS AND STRENGTHS

Injection: 40 mg/2 mL (20 mg/mL), 100 mg/5 mL (20 mg/mL), and 300 mg/15 mL (20 mg/mL) sterile, pale yellow, clear, aqueous solution in a single-dose vial.

4 CONTRAINDICATIONS

- CAMPTOSAR Injection is contraindicated in patients with a known hypersensitivity to the drug or its excipients.

5 WARNINGS AND PRECAUTIONS

5.1 Diarrhea and Cholinergic Reactions

Early diarrhea (occurring during or shortly after infusion of CAMPTOSAR) is usually transient and infrequently severe. It may be accompanied by cholinergic symptoms of rhinitis, increased salivation, miosis, lacrimation, diaphoresis, flushing, and intestinal hyperperistalsis that can cause abdominal cramping. Bradycardia may also occur. Early diarrhea and other cholinergic symptoms may be prevented or treated. Consider prophylactic or therapeutic administration of 0.25 mg to 1 mg of intravenous or subcutaneous atropine (unless clinically contraindicated). These symptoms are expected to occur more frequently with higher irinotecan doses.

Late diarrhea (generally occurring more than 24 hours after administration of CAMPTOSAR) can be life threatening since it may be prolonged and may lead to dehydration, electrolyte imbalance, or sepsis. Grade 3–4 late diarrhea occurred in 23–31% of patients receiving weekly dosing. In the clinical studies, the median time to the onset of late diarrhea was 5 days with 3-week dosing and 11 days with weekly dosing. Late diarrhea can be complicated by colitis, ulceration, bleeding, ileus, obstruction, and infection. Cases of megacolon and intestinal perforation have been reported. Patients should have loperamide readily available to begin treatment for late diarrhea. Begin loperamide at the first episode of poorly formed or loose stools or the earliest onset of bowel movements more frequent than normal. One dosage regimen for loperamide is 4 mg at the first onset of late diarrhea and then 2 mg every 2 hours until the patient is diarrhea-free for at least 12 hours. Loperamide is not recommended to be used for more than 48 consecutive hours at these doses, because of the risk of paralytic ileus. During the night, the patient may take 4 mg of loperamide every 4 hours. Monitor and replace fluid and electrolytes. Use antibiotic support for ileus, fever, or severe neutropenia. Subsequent weekly chemotherapy treatments should be delayed in patients until return of pretreatment bowel function for at least 24 hours without anti-diarrhea medication. Patients must not be treated with CAMPTOSAR until resolution of the bowel obstruction. If grade 2, 3, or 4 late diarrhea recurs, subsequent doses of CAMPTOSAR should be decreased [see Dosage and Administration (2)].

Avoid diuretics or laxatives in patients with diarrhea.

5.2 Myelosuppression

CAMPTOSAR can cause severe myelosuppression. Bacterial, viral, and fungal infections have occurred in patients treated with CAMPTOSAR.

Deaths due to sepsis following severe neutropenia have been reported in patients treated with CAMPTOSAR. In the clinical studies evaluating the weekly dosage schedule, neutropenic fever (concurrent NCI grade 4 neutropenia and fever of grade 2 or greater) occurred in 3% of the patients; 6% of patients received G-CSF for the treatment of neutropenia. Manage febrile neutropenia promptly with antibiotic support [see Warnings and Precautions (5.2)]. Hold CAMPTOSAR if neutropenic fever occurs or if the absolute neutrophil count drops <1000/mm^3. After recovery to an absolute neutrophil count ≥1000/mm^3, subsequent doses of CAMPTOSAR should be reduced [see Dosage and Administration (2)].

When evaluated in the trials of weekly administration, the frequency of grade 3 and 4 neutropenia was higher in patients who received previous pelvic/abdominal irradiation than in those who had not received such irradiation (48% [13/27] versus 24% [67/277]; p=0.04). Patients who have previously received pelvic/abdominal irradiation are at increased risk of severe myelosuppression following the administration of CAMPTOSAR. Based on sparse available data, the concurrent administration of CAMPTOSAR with irradiation is not recommended.

Patients with baseline serum total bilirubin levels of 1.0 mg/dL or more also had a greater likelihood of experiencing first-cycle grade 3 or 4 neutropenia than those with bilirubin levels that were less than 1.0 mg/dL (50% [19/38] versus 18% [47/266]; p<0.001). Patients with deficient glucuronidation of bilirubin, such as those with Gilbert's syndrome, may be at greater risk of myelosuppression when receiving therapy with CAMPTOSAR [see Warnings and Precautions (5.3)].

5.3 Increased Risk of Neutropenia in Patients With Reduced UGT1A1 Activity

Published studies have shown that individuals who are homozygous for either the UGT1A1*28 or *6 alleles (*28/*28, *6/*6) or who are compound or double heterozygous for the UGT1A1*28 and *6 alleles (*6/*28) are at increased risk for severe or life-threatening neutropenia during treatment with CAMPTOSAR. These individuals are UGT1A1 poor metabolizers and experience increased systemic exposure to SN-38, an active metabolite of irinotecan. Individuals who are heterozygous for either the UGT1A1*28 or *6 alleles (*1/*28, *1/*6) are intermediate metabolizers and may also have an increased risk of severe or life-threatening neutropenia [see Dosage and Administration (2) and Clinical Pharmacology (12.3, 12.5)].

Consider UGT1A1 genotype testing for the *28 and *6 alleles to determine UGT1A1 metabolizer status [see Clinical Pharmacology (12.5)].

When administering CAMPTOSAR, consider a reduction in the CAMPTOSAR starting dose by at least one level for patients known to be homozygous or compound heterozygous for the UGT1A1*28 and/or *6 alleles (*28/*28, *6/*6, *6/*28).

Closely monitor patients with UGT1A1 *28 or *6 alleles for neutropenia during and after treatment with CAMPTOSAR. The precise dosage reduction in this patient population is not known. Subsequent dosage modifications may be required based on individual patient tolerance to treatment [see Dosage and Administration (2.1, 2.2)].

5.4 Hypersensitivity

Hypersensitivity reactions including severe anaphylactic or anaphylactoid reactions have been observed. Discontinue CAMPTOSAR if anaphylactic reaction occurs.

5.5 Renal Impairment/Renal Failure

Renal impairment and acute renal failure have been identified, usually in patients who became volume depleted from severe vomiting and/or diarrhea.

5.6 Pulmonary Toxicity

Interstitial Pulmonary Disease (IPD)-like events, including fatalities, have occurred in patients receiving irinotecan (in combination and as monotherapy). Risk factors include pre-existing lung disease, use of pneumotoxic drugs, radiation therapy, and colony stimulating factors. Patients with risk factors should be closely monitored for respiratory symptoms before and during CAMPTOSAR therapy. In Japanese studies, a reticulonodular pattern on chest x-ray was observed in a small percentage of patients. New or progressive, dyspnea, cough, and fever should prompt interruption of chemotherapy, pending diagnostic evaluation. If IPD is diagnosed, CAMPTOSAR and other chemotherapy should be discontinued and appropriate treatment instituted as needed [see Adverse Reactions (6.1)].

5.7 Toxicity of the 5 Day Regimen

Outside of a well-designed clinical study, CAMPTOSAR Injection should not be used in combination with a regimen of 5-FU/LV administered for 4–5 consecutive days every 4 weeks because of reports of increased toxicity, including toxic deaths. CAMPTOSAR should be used as recommended in Table 2 [see Dosage and Administration (2)].

5.8 Increased Toxicity in Patients With Performance Status 2

In patients receiving either irinotecan/5-FU/LV or 5-FU/LV in the clinical trials, higher rates of hospitalization, neutropenic fever, thromboembolism, first-cycle treatment discontinuation, and early deaths were observed in patients with a baseline performance status of 2 than in patients with a baseline performance status of 0 or 1.

5.9 Embryo-Fetal Toxicity

Based on its mechanism of action and findings in animals, CAMPTOSAR can cause fetal harm when administered to a pregnant woman. In animal studies, intravenous administration of irinotecan during the period of organogenesis resulted in embryofetal mortality and teratogenicity in pregnant animals at exposures lower than the human exposure based on area under the curve (AUC) at the clinical dose of 125 mg/m^2. Advise pregnant women of the potential risk to a fetus.

Advise female patients of reproductive potential to avoid becoming pregnant and to use highly effective contraception during treatment with CAMPTOSAR and for 6 months after the final dose. Advise male patients with female partners of reproductive potential to use condoms during treatment and for 3 months after the final dose of CAMPTOSAR [see Use in Specific Populations (8.1), (8.3) and Nonclinical Toxicology (13.1)].

5.10 Patients With Hepatic Impairment

The use of CAMPTOSAR in patients with significant hepatic impairment has not been established. In clinical trials of either dosing schedule, irinotecan was not administered to patients with serum bilirubin >2.0 mg/dL, or transaminase >3 times the upper limit of normal if no liver metastasis, or transaminase >5 times the upper limit of normal with liver metastasis. In clinical trials of the weekly dosage schedule, patients with modestly elevated baseline serum total bilirubin levels (1.0 to 2.0 mg/dL) had a significantly greater likelihood of experiencing first-cycle, grade 3 or 4 neutropenia than those with bilirubin levels that were less than 1.0 mg/dL (50% [19/38] versus 18% [47/226]; p<0.001) [see Dosage and Administration (2.1), Use in Specific Populations (8.7) and Clinical Pharmacology (12.3)].

6 ADVERSE REACTIONS

6.1 Clinical Studies Experience

Because clinical trials are conducted under widely varying conditions, adverse reaction rates observed in the clinical trials of a drug cannot be directly compared to rates in the clinical trials of another drug and may not reflect the rates observed in clinical practice.

Common adverse reactions (≥30%) observed in combination therapy clinical studies are: nausea, vomiting, abdominal pain, diarrhea, constipation, anorexia, mucositis, neutropenia, leukopenia (including lymphocytopenia), anemia, thrombocytopenia, asthenia, pain, fever, infection, abnormal bilirubin, and alopecia.

Common adverse reactions (≥30%) observed in single agent therapy clinical studies are: nausea, vomiting, abdominal pain, diarrhea, constipation, anorexia, neutropenia, leukopenia (including lymphocytopenia), anemia, asthenia, fever, body weight decreasing, and alopecia.

First-Line Combination Therapy

A total of 955 patients with metastatic colorectal cancer received the recommended regimens of irinotecan in combination with 5-FU/LV, 5-FU/LV alone, or irinotecan alone. In the two phase 3 studies, 370 patients received irinotecan in combination with 5-FU/LV, 362 patients received 5-FU/LV alone, and 223 patients received irinotecan alone [see Dosage and Administration (2)].

In Study 1, 49 (7.3%) patients died within 30 days of last study treatment: 21 (9.3%) received irinotecan in combination with 5-FU/LV, 15 (6.8%) received 5-FU/LV alone, and 13 (5.8%) received irinotecan alone. Deaths potentially related to treatment occurred in 2 (0.9%) patients who received irinotecan in combination with 5-FU/LV (2 neutropenic fever/sepsis), 3 (1.4%) patients who received 5-FU/LV alone (1 neutropenic fever/sepsis, 1 CNS bleeding during thrombocytopenia, 1 unknown) and 2 (0.9%) patients who received irinotecan alone (2 neutropenic fever). Deaths from any cause within 60 days of first study treatment were reported for 15 (6.7%) patients who received irinotecan in combination with 5-FU/LV, 16 (7.3%) patients who received 5-FU/LV alone, and 15 (6.7%) patients who received irinotecan alone. Discontinuations due to adverse events were reported for 17 (7.6%) patients who received irinotecan in combination with 5FU/LV, 14 (6.4%) patients who received 5-FU/LV alone, and 26 (11.7%) patients who received irinotecan alone.

In Study 2, 10 (3.5%) patients died within 30 days of last study treatment: 6 (4.1%) received irinotecan in combination with 5-FU/LV and 4 (2.8%) received 5-FU/LV alone. There was one potentially treatment-related death, which occurred in a patient who received irinotecan in combination with 5-FU/LV (0.7%, neutropenic sepsis). Deaths from any cause within 60 days of first study treatment were reported for 3 (2.1%) patients who received irinotecan in combination with 5-FU/LV and 2 (1.4%) patients who received 5-FU/LV alone. Discontinuations due to adverse events were reported for 9 (6.2%) patients who received irinotecan in combination with 5FU/LV and 1 (0.7%) patient who received 5-FU/LV alone.

The most clinically significant adverse events for patients receiving irinotecan-based therapy were diarrhea, nausea, vomiting, neutropenia, and alopecia. The most clinically significant adverse events for patients receiving 5-FU/LV therapy were diarrhea, neutropenia, neutropenic fever, and mucositis. In Study 1, grade 4 neutropenia, neutropenic fever (defined as grade 2 fever and grade 4 neutropenia), and mucositis were observed less often with weekly irinotecan/5-FU/LV than with monthly administration of 5-FU/LV.

Tables 5 and 6 list the clinically relevant adverse events reported in Studies 1 and 2, respectively.

Table 5. Study 1: Percent (%) of Patients Experiencing Clinically Relevant Adverse Events in Combination Therapies [Severity of adverse events based on NCI CTC (version 1.0)]
Adverse Event | Study 1
Adverse Event | Irinotecan + Bolus 5-FU/LV weekly × 4 every 6 weeks N=225 |  | Bolus 5-FU/LV daily × 5 every 4 weeks N=219 |  | Irinotecan weekly × 4 every 6 weeks N=223
Adverse Event | Grade 1–4 | Grade 3&4 | Grade 1–4 | Grade 3&4 | Grade 1–4 | Grade 3&4
TOTAL Adverse Events | 100 | 53.3 | 100 | 45.7 | 99.6 | 45.7
GASTROINTESTINAL
Diarrhea
Late | 84.9 | 22.7 | 69.4 | 13.2 | 83.0 | 31.0
grade 3 | -- | 15.1 | -- | 5.9 | -- | 18.4
grade 4 | -- | 7.6 | -- | 7.3 | -- | 12.6
Early | 45.8 | 4.9 | 31.5 | 1.4 | 43.0 | 6.7
Nausea | 79.1 | 15.6 | 67.6 | 8.2 | 81.6 | 16.1
Abdominal pain | 63.1 | 14.6 | 50.2 | 11.5 | 67.7 | 13.0
Vomiting | 60.4 | 9.7 | 46.1 | 4.1 | 62.8 | 12.1
Anorexia | 34.2 | 5.8 | 42.0 | 3.7 | 43.9 | 7.2
Constipation | 41.3 | 3.1 | 31.5 | 1.8 | 32.3 | 0.4
Mucositis | 32.4 | 2.2 | 76.3 | 16.9 | 29.6 | 2.2
HEMATOLOGIC
Neutropenia | 96.9 | 53.8 | 98.6 | 66.7 | 96.4 | 31.4
grade 3 | -- | 29.8 | -- | 23.7 | -- | 19.3
grade 4 | -- | 24.0 | -- | 42.5 | -- | 12.1
Leukopenia | 96.9 | 37.8 | 98.6 | 23.3 | 96.4 | 21.5
Anemia | 96.9 | 8.4 | 98.6 | 5.5 | 96.9 | 4.5
Neutropenic fever | -- | 7.1 | -- | 14.6 | -- | 5.8
Thrombocytopenia | 96.0 | 2.6 | 98.6 | 2.7 | 96.0 | 1.7
Neutropenic infection | -- | 1.8 | -- | 0 | -- | 2.2
BODY AS A WHOLE
Asthenia | 70.2 | 19.5 | 64.4 | 11.9 | 69.1 | 13.9
Pain | 30.7 | 3.1 | 26.9 | 3.6 | 22.9 | 2.2
Fever | 42.2 | 1.7 | 32.4 | 3.6 | 43.5 | 0.4
Infection | 22.2 | 0 | 16.0 | 1.4 | 13.9 | 0.4
METABOLIC & NUTRITIONAL
Bilirubin | 87.6 | 7.1 | 92.2 | 8.2 | 83.9 | 7.2
DERMATOLOGIC
Exfoliative dermatitis | 0.9 | 0 | 3.2 | 0.5 | 0 | 0
Rash | 19.1 | 0 | 26.5 | 0.9 | 14.3 | 0.4
Alopecia [Complete hair loss = Grade 2] | 43.1 | -- | 26.5 | -- | 46.1 | --
RESPIRATORY
Dyspnea | 27.6 | 6.3 | 16.0 | 0.5 | 22.0 | 2.2
Cough | 26.7 | 1.3 | 18.3 | 0 | 20.2 | 0.4
Pneumonia | 6.2 | 2.7 | 1.4 | 1.0 | 3.6 | 1.3
NEUROLOGIC
Dizziness | 23.1 | 1.3 | 16.4 | 0 | 21.1 | 1.8
Somnolence | 12.4 | 1.8 | 4.6 | 1.8 | 9.4 | 1.3
Confusion | 7.1 | 1.8 | 4.1 | 0 | 2.7 | 0
CARDIOVASCULAR
Vasodilatation | 9.3 | 0.9 | 5.0 | 0 | 9.0 | 0
Hypotension | 5.8 | 1.3 | 2.3 | 0.5 | 5.8 | 1.7
Thromboembolic events [Includes angina pectoris, arterial thrombosis, cerebral infarct, cerebrovascular accident, deep thrombophlebitis, embolus lower extremity, heart arrest, myocardial infarct, myocardial ischemia, peripheral vascular disorder, pulmonary embolus, sudden death, thrombophlebitis, thrombosis, vascular disorder.] | 9.3 | -- | 11.4 | -- | 5.4 | --

Table 6. Study 2: Percent (%) of Patients Experiencing Clinically Relevant Adverse Events in Combination Therapies [Severity of adverse events based on NCI CTC (version 1.0)]
Adverse Event | Study 2
Adverse Event | Irinotecan + 5-FU/LV infusional days 1&2 every 2 weeks N= 145 |  | 5-FU/LV infusional days 1&2 every 2 weeks N=143
Adverse Event | Grades 1–4 | Grades 3&4 | Grades 1–4 | Grades 3&4
TOTAL Adverse Events | 100 | 72.4 | 100 | 39.2
GASTROINTESTINAL
Diarrhea
late | 72.4 | 14.4 | 44.8 | 6.3
grade 3 | -- | 10.3 | -- | 4.2
grade 4 | -- | 4.1 | -- | 2.1
Cholinergic syndrome [Includes rhinitis, increased salivation, miosis, lacrimation, diaphoresis, flushing, abdominal cramping or diarrhea (occurring during or shortly after infusion of irinotecan)] | 28.3 | 1.4 | 0.7 | 0
Nausea | 66.9 | 2.1 | 55.2 | 3.5
Abdominal pain | 17.2 | 2.1 | 16.8 | 0.7
Vomiting | 44.8 | 3.5 | 32.2 | 2.8
Anorexia | 35.2 | 2.1 | 18.9 | 0.7
Constipation | 30.3 | 0.7 | 25.2 | 1.4
Mucositis | 40.0 | 4.1 | 28.7 | 2.8
HEMATOLOGIC
Neutropenia | 82.5 | 46.2 | 47.9 | 13.4
grade 3 | -- | 36.4 | -- | 12.7
grade 4 | -- | 9.8 | -- | 0.7
Leukopenia | 81.3 | 17.4 | 42.0 | 3.5
Anemia | 97.2 | 2.1 | 90.9 | 2.1
Neutropenic fever | -- | 3.4 | -- | 0.7
Thrombocytopenia | 32.6 | 0 | 32.2 | 0
Neutropenic infection | -- | 2.1 | -- | 0
BODY AS A WHOLE
Asthenia | 57.9 | 9.0 | 48.3 | 4.2
Pain | 64.1 | 9.7 | 61.5 | 8.4
Fever | 22.1 | 0.7 | 25.9 | 0.7
Infection | 35.9 | 7.6 | 33.6 | 3.5
METABOLIC AND NUTRITIONAL
Bilirubin | 19.1 | 3.5 | 35.9 | 10.6
DERMATOLOGIC
Hand and foot syndrome | 10.3 | 0.7 | 12.6 | 0.7
Cutaneous signs | 17.2 | 0.7 | 20.3 | 0
Alopecia [Complete hair loss = Grade 2] | 56.6 | -- | 16.8 | --
RESPIRATORY
Dyspnea | 9.7 | 1.4 | 4.9 | 0
CARDIOVASCULAR
Hypotension | 3.4 | 1.4 | 0.7 | 0
Thromboembolic events [Includes angina pectoris, arterial thrombosis, cerebral infarct, cerebrovascular accident, deep thrombophlebitis, embolus lower extremity, heart arrest, myocardial infarct, myocardial ischemia, peripheral vascular disorder, pulmonary embolus, sudden death, thrombophlebitis, thrombosis, vascular disorder.] | 11.7 | -- | 5.6 | --

Second-Line Single-Agent Therapy

Weekly Dosage Schedule

In three clinical studies evaluating the weekly dosage schedule, 304 patients with metastatic carcinoma of the colon or rectum that had recurred or progressed following 5-FU-based therapy were treated with CAMPTOSAR. Seventeen of the patients died within 30 days of the administration of CAMPTOSAR; in five cases (1.6%, 5/304), the deaths were potentially drug-related. One of the patients died of neutropenic sepsis without fever. Neutropenic fever occurred in nine (3.0%) other patients; these patients recovered with supportive care.

One hundred nineteen (39.1%) of the 304 patients were hospitalized because of adverse events; 81 (26.6%) patients were hospitalized for events judged to be related to administration of CAMPTOSAR. The primary reasons for drug-related hospitalization were diarrhea, with or without nausea and/or vomiting (18.4%); neutropenia/leukopenia, with or without diarrhea and/or fever (8.2%); and nausea and/or vomiting (4.9%).

The first dose of at least one cycle of CAMPTOSAR was reduced for 67% of patients who began the studies at the 125-mg/m^2 starting dose. Within-cycle dose reductions were required for 32% of the cycles initiated at the 125-mg/m^2 dose level. The most common reasons for dose reduction were late diarrhea, neutropenia, and leukopenia. Thirteen (4.3%) patients discontinued treatment with CAMPTOSAR because of adverse events. The adverse events in Table 7 are based on the experience of the 304 patients enrolled in the three studies described in Clinical Studies (14.1).

Table 7. Adverse Events Occurring in >10% of 304 Previously Treated Patients With Metastatic Carcinoma of the Colon or Rectum [Severity of adverse events based on NCI CTC (version 1.0)]
 | % of Patients Reporting
Body System & Event | NCI Grades 1–4 | NCI Grades 3 & 4
GASTROINTESTINAL
Diarrhea (late) [Occurring >24 hours after administration of CAMPTOSAR] | 88 | 31
7–9 stools/day (grade 3) | — | (16)
≥10 stools/day (grade 4) | — | (14)
Nausea | 86 | 17
Vomiting | 67 | 12
Anorexia | 55 | 6
Diarrhea (early) [Occurring ≤24 hours after administration of CAMPTOSAR] | 51 | 8
Constipation | 30 | 2
Flatulence | 12 | 0
Stomatitis | 12 | 1
Dyspepsia | 10 | 0
HEMATOLOGIC
Leukopenia | 63 | 28
Anemia | 60 | 7
Neutropenia | 54 | 26
500 to <1000/mm^3 (grade 3) | — | (15)
<500/mm^3 (grade 4) | — | (12)
BODY AS A WHOLE
Asthenia | 76 | 12
Abdominal cramping/pain | 57 | 16
Fever | 45 | 1
Pain | 24 | 2
Headache | 17 | 1
Back pain | 14 | 2
Chills | 14 | 0
Minor infection [Primarily upper respiratory infections] | 14 | 0
Edema | 10 | 1
Abdominal enlargement | 10 | 0
METABOLIC AND NUTRITIONAL
↓ Body weight | 30 | 1
Dehydration | 15 | 4
↑ Alkaline phosphatase | 13 | 4
↑ SGOT | 10 | 1
DERMATOLOGIC
Alopecia | 60 | NA [Not applicable; complete hair loss = NCI grade 2]
Sweating | 16 | 0
Rash | 13 | 1
RESPIRATORY
Dyspnea | 22 | 4
↑ Coughing | 17 | 0
Rhinitis | 16 | 0
NEUROLOGIC
Insomnia | 19 | 0
Dizziness | 15 | 0
CARDIOVASCULAR
Vasodilation (flushing) | 11 | 0

Once-Every-3-Week Dosage Schedule

A total of 535 patients with metastatic colorectal cancer whose disease had recurred or progressed following prior 5-FU therapy participated in the two phase 3 studies: 316 received irinotecan, 129 received 5-FU, and 90 received best supportive care. Eleven (3.5%) patients treated with irinotecan died within 30 days of treatment. In three cases (1%, 3/316), the deaths were potentially related to irinotecan treatment and were attributed to neutropenic infection, grade 4 diarrhea, and asthenia, respectively. One (0.8%, 1/129) patient treated with 5-FU died within 30 days of treatment; this death was attributed to grade 4 diarrhea.

Hospitalizations due to serious adverse events occurred at least once in 60% (188/316) of patients who received irinotecan, 63% (57/90) who received best supportive care, and 39% (50/129) who received 5-FU-based therapy. Eight percent of patients treated with irinotecan and 7% treated with 5-FU-based therapy discontinued treatment due to adverse events.

Of the 316 patients treated with irinotecan, the most clinically significant adverse events (all grades, 1–4) were diarrhea (84%), alopecia (72%), nausea (70%), vomiting (62%), cholinergic symptoms (47%), and neutropenia (30%). Table 8 lists the grade 3 and 4 adverse events reported in the patients enrolled to all treatment arms of the two studies described in Clinical Studies (14.1).

Table 8. Percent Of Patients Experiencing Grade 3 & 4 Adverse Events In Comparative Studies Of Once-Every-3-Week Irinotecan Therapy [Severity of adverse events based on NCI CTC (version 1.0)]
 | Study 1 |  | Study 2
Adverse Event | Irinotecan N=189 | BSC [BSC = best supportive care] N=90 | Irinotecan N=127 | 5-FU N=129
TOTAL Grade 3/4 Adverse Events | 79 | 67 | 69 | 54
GASTROINTESTINAL
Diarrhea | 22 | 6 | 22 | 11
Vomiting | 14 | 8 | 14 | 5
Nausea | 14 | 3 | 11 | 4
Abdominal pain | 14 | 16 | 9 | 8
Constipation | 10 | 8 | 8 | 6
Anorexia | 5 | 7 | 6 | 4
Mucositis | 2 | 1 | 2 | 5
HEMATOLOGIC
Leukopenia/Neutropenia | 22 | 0 | 14 | 2
Anemia | 7 | 6 | 6 | 3
Hemorrhage | 5 | 3 | 1 | 3
Thrombocytopenia | 1 | 0 | 4 | 2
Infection
without grade 3/4 neutropenia | 8 | 3 | 1 | 4
with grade 3/4 neutropenia | 1 | 0 | 2 | 0
Fever
without grade 3/4 neutropenia | 2 | 1 | 2 | 0
with grade 3/4 neutropenia | 2 | 0 | 4 | 2
BODY AS A WHOLE
Pain | 19 | 22 | 17 | 13
Asthenia | 15 | 19 | 13 | 12
METABOLIC AND NUTRITIONAL
Hepatic [Hepatic includes events such as ascites and jaundice] | 9 | 7 | 9 | 6
DERMATOLOGIC
Hand and foot syndrome | 0 | 0 | 0 | 5
Cutaneous signs [Cutaneous signs include events such as rash] | 2 | 0 | 1 | 3
RESPIRATORY [Respiratory includes events such as dyspnea and cough] | 10 | 8 | 5 | 7
NEUROLOGIC [Neurologic includes events such as somnolence] | 12 | 13 | 9 | 4
CARDIOVASCULAR [Cardiovascular includes events such as dysrhythmias, ischemia, and mechanical cardiac dysfunction] | 9 | 3 | 4 | 2
OTHER [Other includes events such as accidental injury, hepatomegaly, syncope, vertigo, and weight loss] | 32 | 28 | 12 | 14

The incidence of akathisia in clinical trials of the weekly dosage schedule was greater (8.5%, 4/47 patients) when prochlorperazine was administered on the same day as CAMPTOSAR than when these drugs were given on separate days (1.3%, 1/80 patients). The 8.5% incidence of akathisia, however, is within the range reported for use of prochlorperazine when given as a premedication for other chemotherapies.

6.2 Postmarketing Experience

The following adverse reactions have been identified during post approval use of CAMPTOSAR. Because these reactions are reported voluntarily from a population of uncertain size, it is not always possible to reliably estimate their frequency or establish a causal relationship to drug exposure.

Myocardial ischemic events have been observed following CAMPTOSAR therapy. Thromboembolic events have been observed in patients receiving CAMPTOSAR.

Symptomatic pancreatitis, asymptomatic pancreatic enzyme elevation have been reported. Increases in serum levels of transaminases (i.e., AST and ALT) in the absence of progressive liver metastasis have been observed.

Hyponatremia, mostly with diarrhea and vomiting, has been reported.

Transient dysarthria has been reported in patients treated with CAMPTOSAR; in some cases, the event was attributed to the cholinergic syndrome observed during or shortly after infusion of irinotecan.

Interaction between CAMPTOSAR and neuromuscular blocking agents cannot be ruled out. Irinotecan has anticholinesterase activity, which may prolong the neuromuscular blocking effects of suxamethonium and the neuromuscular blockade of non-depolarizing drugs may be antagonized.

Infections: fungal and viral infections have been reported.

7 DRUG INTERACTIONS

7.1 5-Fluorouracil (5-FU) and Leucovorin (LV)

In a phase 1 clinical study involving irinotecan, 5-fluorouracil (5-FU), and leucovorin (LV) in 26 patients with solid tumors, the disposition of irinotecan was not substantially altered when the drugs were co-administered. Although the Cmax and AUC0–24 of SN-38, the active metabolite, were reduced (by 14% and 8%, respectively) when irinotecan was followed by 5-FU and LV administration compared with when irinotecan was given alone, this sequence of administration was used in the combination trials and is recommended [see Dosage and Administration (2)]. Formal in vivo or in vitro drug interaction studies to evaluate the influence of irinotecan on the disposition of 5-FU and LV have not been conducted.

7.2 Strong CYP3A4 Inducers

Exposure to irinotecan or its active metabolite SN-38 is substantially reduced in adult and pediatric patients concomitantly receiving the CYP3A4 enzyme-inducing anticonvulsants phenytoin, phenobarbital, carbamazepine, or St. John's wort. The appropriate starting dose for patients taking these or other strong inducers such as rifampin and rifabutin has not been defined. Consider substituting non-enzyme inducing therapies at least 2 weeks prior to initiation of CAMPTOSAR therapy. Do not administer strong CYP3A4 inducers with CAMPTOSAR unless there are no therapeutic alternatives.

7.3 Strong CYP3A4 or UGT1A1 Inhibitors

Irinotecan and its active metabolite, SN-38, are metabolized via the human cytochrome P450 3A4 isoenzyme (CYP3A4) and uridine diphosphate-glucuronosyl transferase 1A1 (UGT1A1), respectively, [see Clinical Pharmacology (12.3)]. Patients receiving concomitant ketoconazole, a CYP3A4 and UGT1A1 inhibitor, have increased exposure to irinotecan and its active metabolite SN-38. Coadministration of CAMPTOSAR with other inhibitors of CYP3A4 (e.g., clarithromycin, indinavir, itraconazole, lopinavir, nefazodone, nelfinavir, ritonavir, saquinavir, telaprevir, voriconazole) or UGT1A1 (e.g., atazanavir, gemfibrozil, indinavir) may increase systemic exposure to irinotecan or SN-38. Discontinue strong CYP3A4 inhibitors at least 1 week prior to starting CAMPTOSAR therapy. Do not administer strong CYP3A4 or UGT1A1 inhibitors with CAMPTOSAR unless there are no therapeutic alternatives.

8 USE IN SPECIFIC POPULATIONS

8.1 Pregnancy

Risk Summary

Based on findings from animal studies and its mechanism of action, CAMPTOSAR can cause fetal harm when administered to a pregnant woman [see Clinical Pharmacology (12.1)]. Available postmarketing and published data reporting the use of CAMPTOSAR in pregnant women, are insufficient and confounded by the concomitant use of other cytotoxic drugs, to evaluate for any drug-associated risk for major birth defects, miscarriage, or adverse maternal or fetal outcomes. In animal studies, intravenous administration of irinotecan to rats and rabbits during the period of organogenesis resulted in embryofetal mortality and teratogenicity in pregnant animals at exposures lower than the human exposure based on AUC at the clinical dose of 125 mg/m^2 (see Data). Advise pregnant women of the potential risk to a fetus.

In the U.S. general population, the estimated background risk of major birth defects and miscarriage in clinically recognized pregnancies is 2 to 4% and 15 to 20%, respectively.

Data

Animal Data

Radioactivity related to ^14C-irinotecan crosses the placenta of rats following intravenous administration. Intravenous administration of irinotecan to rats at a dose of 6 mg/kg/day (approximately 0.2 times the clinical exposure (AUC) at the 125 mg/m^2 dose based on exposure data from a separate rat study) during the period of organogenesis resulted in increased post-implantation loss and decreased numbers of live fetuses; at doses ≥ 1.2 mg/kg/day (approximately 0.03 times the clinical exposure (AUC) at the 125 mg/m^2 dose based on exposure data from a separate rat study) there were increases in a variety of external, visceral, and skeletal abnormalities. Administration of irinotecan to pregnant rabbits at a dose of 6 mg/kg (approximately half of the clinical dose of 125 mg/m^2 based on BSA) resulted in similar findings to those in rats, with increased post-implantation loss, decreased live fetuses, and increased external, visceral, and skeletal abnormalities.

Irinotecan administered to rat dams for the period following organogenesis through weaning at doses of 6 mg/kg/day caused decreased learning ability and decreased female body weights in the offspring.

8.2 Lactation

Risk Summary

Irinotecan and its metabolites are present in human milk. There is no information regarding the effects of irinotecan on the breastfed infant, or on milk production. Because of the potential for serious adverse reactions from CAMPTOSAR in the breastfed child, advise lactating women not to breastfeed during treatment with CAMPTOSAR and for 7 days after the final dose.

8.3 Females and Males of Reproductive Potential

Pregnancy Testing

Verify the pregnancy status in female patients of reproductive potential prior to initiating CAMPTOSAR.

Contraception

CAMPTOSAR can cause fetal harm when administered to a pregnant woman.

Females

Advise female patients of reproductive potential to use effective contraception during treatment and for 6 months after the final dose of CAMPTOSAR [see Use in Specific Populations (8.1) and Nonclinical Toxicology (13.1)].

Males

Due to the potential for genotoxicity, advise male patients with female partners of reproductive potential to use condoms during treatment and for 3 months after the final dose of CAMPTOSAR [see Nonclinical Toxicology (13.1)].

Infertility

Females

Based on postmarketing reports, female fertility may be impaired by treatment with CAMPTOSAR. Menstrual dysfunction has been reported following CAMPTOSAR administration.

Males

Based on findings from animal studies, male fertility may be impaired by treatment with CAMPTOSAR [see Nonclinical Toxicology (13.1)].

8.4 Pediatric Use

The effectiveness of irinotecan in pediatric patients has not been established. Results from two open-label, single arm studies were evaluated. One hundred and seventy children with refractory solid tumors were enrolled in one phase 2 trial in which 50 mg/ m^2 of irinotecan was infused for 5 consecutive days every 3 weeks. Grade 3–4 neutropenia was experienced by 54 (31.8%) patients. Neutropenia was complicated by fever in 15 (8.8%) patients. Grade 3–4 diarrhea was observed in 35 (20.6%) patients. This adverse event profile was comparable to that observed in adults. In the second phase 2 trial of 21 children with previously untreated rhabdomyosarcoma, 20 mg/m^2 of irinotecan was infused for 5 consecutive days on weeks 0, 1, 3 and 4. This single agent therapy was followed by multimodal therapy. Accrual to the single agent irinotecan phase was halted due to the high rate (28.6%) of progressive disease and the early deaths (14%). The adverse event profile was different in this study from that observed in adults; the most significant grade 3 or 4 adverse events were dehydration experienced by 6 patients (28.6%) associated with severe hypokalemia in 5 patients (23.8%) and hyponatremia in 3 patients (14.3%); in addition Grade 3–4 infection was reported in 5 patients (23.8%) (across all courses of therapy and irrespective of causal relationship).

Pharmacokinetic parameters for irinotecan and SN-38 were determined in 2 pediatric solid-tumor trials at dose levels of 50 mg/m^2 (60-min infusion, n=48) and 125 mg/m^2 (90-min infusion, n=6). Irinotecan clearance (mean ± S.D.) was 17.3 ± 6.7 L/h/m^2 for the 50mg/m^2 dose and 16.2 ± 4.6 L/h/m^2 for the 125 mg/m^2 dose, which is comparable to that in adults. Dose-normalized SN-38 AUC values were comparable between adults and children. Minimal accumulation of irinotecan and SN-38 was observed in children on daily dosing regimens [daily × 5 every 3 weeks or (daily × 5) × 2 weeks every 3 weeks].

8.5 Geriatric Use

Patients greater than 65 years of age should be closely monitored because of a greater risk of early and late diarrhea in this population [see Clinical Pharmacology (12.3) and Adverse Reactions (6.1)]. The starting dose of CAMPTOSAR in patients 70 years and older for the once-every-3-week-dosage schedule should be 300 mg/m^2 [see Clinical Pharmacology (12.3) and Dosage and Administration (2)].

The frequency of grade 3 and 4 late diarrhea by age was significantly greater in patients ≥65 years than in patients <65 years (40% [53/133] versus 23% [40/171]; p=0.002). In another study of 183 patients treated on the weekly schedule, the frequency of grade 3 or 4 late diarrhea in patients ≥65 years of age was 28.6% [26/91] and in patients <65 years of age was 23.9% [22/92].

8.6 Renal Impairment

The influence of renal impairment on the pharmacokinetics of irinotecan has not been evaluated. Therefore, use caution in patients with impaired renal function. CAMPTOSAR is not recommended for use in patients on dialysis.

8.7 Hepatic Impairment

Irinotecan clearance is diminished in patients with hepatic impairment while exposure to the active metabolite SN-38 is increased relative to that in patients with normal hepatic function. The magnitude of these effects is proportional to the degree of liver impairment as measured by elevations in total bilirubin and transaminase concentrations. Therefore, use caution when administering CAMPTOSAR to patients with hepatic impairment. The tolerability of irinotecan in patients with hepatic dysfunction (bilirubin greater than 2 mg/dl) has not been assessed sufficiently, and no recommendations for dosing can be made [see Dosage and Administration (2.1), Warnings and Precautions (5.10) and Clinical Pharmacology (12.3)].

10 OVERDOSAGE

In U.S. phase 1 trials, single doses of up to 345 mg/m^2 of irinotecan were administered to patients with various cancers. Single doses of up to 750 mg/m^2 of irinotecan have been given in non-U.S. trials. The adverse events in these patients were similar to those reported with the recommended dosage and regimen. There have been reports of overdosage at doses up to approximately twice the recommended therapeutic dose, which may be fatal. The most significant adverse reactions reported were severe neutropenia and severe diarrhea. There is no known antidote for overdosage of CAMPTOSAR. Maximum supportive care should be instituted to prevent dehydration due to diarrhea and to treat any infectious complications.

11 DESCRIPTION

CAMPTOSAR Injection (irinotecan hydrochloride injection) is an antineoplastic agent of the topoisomerase I inhibitor class.

CAMPTOSAR is supplied as a sterile, pale yellow, clear, aqueous solution. Each milliliter of solution contains 20 mg of irinotecan hydrochloride (on the basis of the trihydrate salt), 45 mg of sorbitol, NF, and 0.9 mg of lactic acid, USP. The pH of the solution has been adjusted to 3.5 (range, 3.0 to 3.8) with sodium hydroxide or hydrochloric acid. CAMPTOSAR is intended for dilution with 5% Dextrose Injection, USP (D5W), or 0.9% Sodium Chloride Injection, USP, prior to intravenous infusion. The preferred diluent is 5% Dextrose Injection, USP.

Irinotecan hydrochloride is a semisynthetic derivative of camptothecin, an alkaloid extract from plants such as Camptotheca acuminata or is chemically synthesized.

The chemical name is (S)-4,11-diethyl-3,4,12,14-tetrahydro-4-hydroxy-3,14-dioxo1H-pyrano[3',4':6,7]-indolizino[1,2-b]quinolin-9-yl-[1,4'bipiperidine]-1'-carboxylate, monohydrochloride, trihydrate. Its empirical formula is C33H38N4O6∙HCl∙3H2O and molecular weight is 677.19. It is slightly soluble in water and organic solvents. Its structural formula is as follows:

12 CLINICAL PHARMACOLOGY

12.1 Mechanism of Action

Irinotecan is a derivative of camptothecin. Camptothecins interact specifically with the enzyme topoisomerase I, which relieves torsional strain in DNA by inducing reversible single-strand breaks. Irinotecan and its active metabolite SN-38 bind to the topoisomerase I-DNA complex and prevent religation of these single-strand breaks. Current research suggests that the cytotoxicity of irinotecan is due to double-strand DNA damage produced during DNA synthesis when replication enzymes interact with the ternary complex formed by topoisomerase I, DNA, and either irinotecan or SN-38. Mammalian cells cannot efficiently repair these double-strand breaks.

12.2 Pharmacodynamics

Irinotecan serves as a water-soluble precursor of the lipophilic metabolite SN-38. SN-38 is formed from irinotecan by carboxylesterase-mediated cleavage of the carbamate bond between the camptothecin moiety and the dipiperidino side chain. SN-38 is approximately 1000 times as potent as irinotecan as an inhibitor of topoisomerase I purified from human and rodent tumor cell lines. In vitro cytotoxicity assays show that the potency of SN-38 relative to irinotecan varies from 2- to 2000-fold; however, the plasma area under the concentration versus time curve (AUC) values for SN-38 are 2% to 8% of irinotecan and SN-38 is 95% bound to plasma proteins compared to approximately 50% bound to plasma proteins for irinotecan [see Clinical Pharmacology (12.3)]. The precise contribution of SN-38 to the activity of CAMPTOSAR is thus unknown. Both irinotecan and SN-38 exist in an active lactone form and an inactive hydroxy acid anion form. A pH-dependent equilibrium exists between the two forms such that an acid pH promotes the formation of the lactone, while a more basic pH favors the hydroxy acid anion form.

Administration of irinotecan has resulted in antitumor activity in mice bearing cancers of rodent origin and in human carcinoma xenografts of various histological types.

12.3 Pharmacokinetics

After intravenous infusion of irinotecan in humans, irinotecan plasma concentrations decline in a multiexponential manner, with a mean terminal elimination half-life of about 6 to 12 hours. The mean terminal elimination half-life of the active metabolite SN-38 is about 10 to 20 hours. The half-lives of the lactone (active) forms of irinotecan and SN-38 are similar to those of total irinotecan and SN-38, as the lactone and hydroxy acid forms are in equilibrium.

Over the recommended dose range of 50 to 350 mg/m^2, the AUC of irinotecan increases linearly with dose; the AUC of SN-38 increases less than proportionally with dose. Maximum concentrations of the active metabolite SN-38 are generally seen within 1 hour following the end of a 90-minute infusion of irinotecan. Pharmacokinetic parameters for irinotecan and SN-38 following a 90-minute infusion of irinotecan at dose levels of 125 and 340 mg/m^2 determined in two clinical studies in patients with solid tumors are summarized in Table 9:

Table 9. Summary of Mean (±Standard Deviation) Irinotecan and SN-38 Pharmacokinetic Parameters in Patients With Solid Tumors
Dose (mg/m^2) | Irinotecan |  |  |  | SN-38
Dose (mg/m^2) | Cmax (ng/mL) | AUC0–24 (ng∙h/mL) | t1/2 (h) | Vz (L/m^2) | CL (L/h/m^2) | Cmax (ng/mL) | AUC0–24 (ng∙h/mL) | t1/2 (h)
125 (N=64) | 1,660 ±797 | 10,200 ±3,270 | 5.8 [Plasma specimens collected for 24 hours following the end of the 90-minute infusion.] ±0.7 | 110 ±48.5 | 13.3 ±6.01 | 26.3 ±11.9 | 229 ±108 | 10.4 ±3.1
340 (N=6) | 3,392 ±874 | 20,604 ±6,027 | 11.7 [Plasma specimens collected for 48 hours following the end of the 90-minute infusion. Because of the longer collection period, these values provide a more accurate reflection of the terminal elimination half-lives of irinotecan and SN-38.] ±1.0 | 234 ±69.6 | 13.9 ±4.0 | 56.0 ±28.2 | 474 ±245 | 21.0 ±4.3
Cmax - Maximum plasma concentration
AUC0–24 - Area under the plasma concentration-time curve from time
0 to 24 hours after the end of the 90-minute infusion
t1/2 - Terminal elimination half-life
Vz - Volume of distribution of terminal elimination phase
CL - Total systemic clearance

Distribution

Irinotecan exhibits moderate plasma protein binding (30% to 68% bound). SN-38 is highly bound to human plasma proteins (approximately 95% bound). The plasma protein to which irinotecan and SN-38 predominantly binds is albumin.

Elimination

Metabolism

Irinotecan is subject to extensive metabolic conversion by various enzyme systems, including esterases that form an active metabolite SN-38, and UGT1A1 which mediates the glucuronidation of SN-38 to form an inactive metabolite. SN-38 glucuronide had 1/50 to 1/100 the activity of SN-38. Patients who are homozygous for either the UGT1A1*28 or *6 alleles, or who are compound heterozygous for these alleles, have higher SN-38 AUC than patients with the wild-type UGT1A1 alleles [see Dosage and Administration (2.3), Warnings and Precautions (5.3), and Clinical Pharmacology (12.5)].

Irinotecan can also undergo CYP3A4-mediated oxidative metabolism to several inactive metabolites, one of which can be hydrolyzed by carboxylesterase to release the active metabolite SN-38.

Excretion

The disposition of irinotecan has not been fully elucidated in humans. The urinary excretion of irinotecan is 11% to 20%; SN-38, <1%; and SN-38 glucuronide, 3%. The cumulative biliary and urinary excretion of irinotecan and its metabolites (SN-38 and SN-38 glucuronide) over a period of 48 hours following administration of irinotecan in two patients ranged from approximately 25% (100 mg/m^2) to 50% (300 mg/m^2).

Specific Populations

Geriatric Patients

The pharmacokinetics of irinotecan administered using the weekly schedule was evaluated in a study of 183 patients that was prospectively designed to investigate the effect of age on irinotecan toxicity. Results from this trial indicate that there are no differences in the pharmacokinetics of irinotecan, SN-38, and SN-38 glucuronide in patients <65 years of age compared with patients ≥65 years of age. In a study of 162 patients that was not prospectively designed to investigate the effect of age, small (less than 18%) but statistically significant differences in dose-normalized irinotecan pharmacokinetic parameters in patients <65 years of age compared to patients ≥65 years of age were observed. Although dose-normalized AUC0–24 for SN-38 in patients ≥65 years of age was 11% higher than in patients <65 years of age, this difference was not statistically significant. No change in the starting dose is recommended for geriatric patients receiving the weekly dosage schedule of irinotecan [see Dosage and Administration (2)].

Male and Female Patients

The pharmacokinetics of irinotecan do not appear to be influenced by gender.

Racial and Ethnic Groups

The influence of race on the pharmacokinetics of irinotecan has not been evaluated.

Patients with Renal Impairment

The influence of renal impairment on the pharmacokinetics of irinotecan has not been evaluated.

Patients with Hepatic Impairment

Irinotecan clearance is diminished in patients with hepatic impairment while exposure to the active metabolite SN-38 is increased relative to that in patients with normal hepatic function. The magnitude of these effects is proportional to the degree of liver impairment as measured by elevations in total bilirubin and transaminase concentrations. However, the tolerability of irinotecan in patients with hepatic dysfunction (bilirubin greater than 2 mg/dl) has not been assessed sufficiently.

Drug Interaction Studies

Clinical Studies and Model-Informed Approaches

Dexamethasone, a moderate CYP3A4 inducer, does not appear to alter the pharmacokinetics of irinotecan.

In Vitro Studies

Irinotecan and the metabolites SN-38 and aminopentane carboxylic acid (APC) do not inhibit cytochrome P-450 isozymes.

12.5 Pharmacogenomics

The active metabolite SN-38 is further metabolized via UGT1A1. Genetic variants of the UGT1A1 gene such as the UGT1A1*28 [(TA)7] and *6 alleles lead to reduced UGT1A1 enzyme expression or activity and decreased function to a similar extent.

Individuals who are homozygous or compound (double) heterozygous for these alleles (e.g., *28/*28, *6/*6, *6/*28) are UGT1A1 poor metabolizers and are at increased risk for severe or life-threatening neutropenia from CAMPTOSAR due to elevated systemic exposure to SN-38. The UGT1A1*6/*6 genotype should not be confused with 6/6 genotype, which is sometimes used to represent the genotype of individuals who are wild type for UGT1A1*28. Individuals who are heterozygous for either the UGT1A1*28 or *6 alleles (*1/*6, *1/*28) are UGT1A1 intermediate metabolizers and may also have an increased risk of severe or life-threatening neutropenia [see Dosage and Administration (2.3), Warnings and Precautions (5.3), and Clinical Pharmacology (12.3)].

Published studies have shown that individuals with UGT1A1*28 and *6 alleles may be at an increased risk of severe diarrhea. The risk evidence appears greater in UGT1A1*28 and *6 homozygous patients and in those taking irinotecan doses > 125 mg/m^2 [see Warnings and Precautions (5.1)].

UGT1A1*28 and *6 alleles occur at various frequencies in different populations. Approximately 20% of Black or African American, 10% of White, and 2% of East Asian individuals are homozygous for the UGT1A1*28 allele. Approximately 2–6 % of East Asian individuals are homozygous for the UGT1A1*6 allele. The UGT1A1*6 allele is uncommon in Black or African American or in White individuals. Decreased function alleles other than UGT1A1*28 and *6 may be present in certain populations.

13 NONCLINICAL TOXICOLOGY

13.1 Carcinogenesis, Mutagenesis, Impairment of Fertility

Long-term carcinogenicity studies with irinotecan were not conducted. Rats were, however, administered intravenous doses of 2 mg/kg or 25 mg/kg irinotecan once per week for 13 weeks (in separate studies, the 25 mg/kg dose produced an irinotecan Cmax and AUC that were about 7.0 times and 1.3 times the respective values in patients administered 125 mg/m^2 weekly) and were then allowed to recover for 91 weeks. Under these conditions, there was a significant linear trend with dose for the incidence of combined uterine horn endometrial stromal polyps and endometrial stromal sarcomas. Irinotecan was clastogenic both in vitro (chromosome aberrations in Chinese hamster ovary cells) and in vivo (micronucleus test in mice). Neither irinotecan nor its active metabolite SN-38 was mutagenic in the in vitro Ames assay.

No significant adverse effects on fertility and general reproductive performance were observed after intravenous administration of irinotecan in doses of up to 6 mg/kg/day to rats and rabbits; however, atrophy of male reproductive organs was observed after multiple daily irinotecan doses both in rodents at 20 mg/kg and in dogs at 0.4 mg/kg. In separate studies in rodents, this dose produced an irinotecan Cmax and AUC about 5 and 1 times, respectively, of the corresponding values in patients administered 125 mg/m^2 weekly. In dogs this dose produced an irinotecan Cmax and AUC about one-half and 1/15th, respectively, of the corresponding values in patients administered 125 mg/m^2 weekly.

14 CLINICAL STUDIES

Irinotecan has been studied in clinical trials in combination with 5-fluorouracil (5-FU) and leucovorin (LV) and as a single agent [see Dosage and Administration (2)]. When given as a component of combination-agent treatment, irinotecan was either given with a weekly schedule of bolus 5-FU/LV or with an every-2-week schedule of infusional 5-FU/LV. Weekly and once-every-3-week dosage schedules were used for the single-agent irinotecan studies. Clinical studies of combination and single-agent use are described below.

14.1 Metastatic Colorectal Cancer

First-Line Therapy in Combination with 5-FU/LV: Studies 1 and 2

Two phase 3, randomized, controlled, multinational clinical trials support the use of CAMPTOSAR Injection as first-line treatment of patients with metastatic carcinoma of the colon or rectum. In each study, combinations of irinotecan with 5-FU and LV were compared with 5-FU and LV alone. Study 1 compared combination irinotecan/bolus 5-FU/LV therapy given weekly with a standard bolus regimen of 5-FU/LV alone given daily for 5 days every 4 weeks; an irinotecan-alone treatment arm given on a weekly schedule was also included. Study 2 evaluated two different methods of administering infusional 5-FU/LV, with or without irinotecan. In both studies, concomitant medications such as antiemetics, atropine, and loperamide were given to patients for prophylaxis and/or management of symptoms from treatment. In Study 2, a 7-day course of fluoroquinolone antibiotic prophylaxis was given in patients whose diarrhea persisted for greater than 24 hours despite loperamide or if they developed a fever in addition to diarrhea. Treatment with oral fluoroquinolone was also initiated in patients who developed an absolute neutrophil count (ANC) <500/mm^3, even in the absence of fever or diarrhea. Patients in both studies also received treatment with intravenous antibiotics if they had persistent diarrhea or fever or if ileus developed.

In both studies, the combination of irinotecan/5-FU/LV therapy resulted in significant improvements in objective tumor response rates, time to tumor progression, and survival when compared with 5-FU/LV alone. These differences in survival were observed in spite of second-line therapy in a majority of patients on both arms, including crossover to irinotecan-containing regimens in the control arm. Patient characteristics and major efficacy results are shown in Table 10.

Table 10. Combination Dosage Schedule: Study Results
 | Study 1 |  |  | Study 2
 | Irinotecan + Bolus 5-FU/LV weekly × 4 every 6 weeks | Bolus 5-FU/LV daily × 5 every 4 weeks | Irinotecan weekly × 4 every 6 weeks | Irinotecan + Infusional 5-FU/LV | Infusional 5-FU/LV
Number of patients | 231 | 226 | 226 | 198 | 187
Demographics and treatment administration
Female/Male (%) | 34/65 | 45/54 | 35/64 | 33/67 | 47/53
Median age in years (range) | 62 (25–85) | 61 (19–85) | 61 (30–87) | 62 (27–75) | 59 (24–75)
Performance status (%)
0 | 39 | 41 | 46 | 51 | 51
1 | 46 | 45 | 46 | 42 | 41
2 | 15 | 13 | 8 | 7 | 8
Primary tumor (%)
Colon | 81 | 85 | 84 | 55 | 65
Rectum | 17 | 14 | 15 | 45 | 35
Median time from diagnosis to randomization (months, range) | 1.9 (0–161) | 1.7 (0–203) | 1.8 (0.1–185) | 4.5 (0–88) | 2.7 (0–104)
Prior adjuvant 5-FU therapy (%) No Yes | 89 11 | 92 8 | 90 10 | 74 26 | 76 24
Median duration of study treatment [Study 1: N=225 (irinotecan/5-FU/LV),N=219 (5-FU/LV),N=223 (irinotecan) Study 2: N=199 (irinotecan/5-FU/LV),N=186 (5-FU/LV)] (months) | 5.5 | 4.1 | 3.9 | 5.6 | 4.5
Median Relative Dose Intensity (%) Irinotecan 5-FU | 72 71 | — 86 | 75 — | 87 86 | — 93
Efficacy Results
Confirmed objective tumor response rate [Confirmed ≥ 4 to 6 weeks after first evidence of objective response] (%) | 39 | 21 | 18 | 35 | 22
Confirmed objective tumor response rate [Confirmed ≥ 4 to 6 weeks after first evidence of objective response] (%) | (p<0.0001) [Chi-square test] |  |  | (p<0.005)
Median time to tumor progression [Log-rank test] (months) | 7.0 | 4.3 | 4.2 | 6.7 | 4.4
Median time to tumor progression [Log-rank test] (months) | (p=0.004) |  |  | (p<0.001)
Median survival (months) | 14.8 | 12.6 | 12.0 | 17.4 | 14.1
Median survival (months) | (p<0.05) |  |  | (p<0.05)

Improvement was noted with irinotecan-based combination therapy relative to 5-FU/LV when response rates and time to tumor progression were examined across the following demographic and disease-related subgroups (age, gender, ethnic origin, performance status, extent of organ involvement with cancer, time from diagnosis of cancer, prior adjuvant therapy, and baseline laboratory abnormalities). Figures 1 and 2 illustrate the Kaplan-Meier survival curves for the comparison of irinotecan/5-FU/LV versus 5-FU/LV in Studies 1 and 2, respectively.

Second-Line Therapy After 5-FU-Based Treatment

4 Weekly Doses on a 6-Week Cycle: Studies 3, 4, and 5

Data from three open-label, single-agent, clinical studies, involving a total of 304 patients in 59 centers, support the use of CAMPTOSAR in the treatment of patients with metastatic cancer of the colon or rectum that has recurred or progressed following treatment with 5-FU-based therapy. These studies were designed to evaluate tumor response rate and do not provide information on effects on survival and disease-related symptoms. In each study, CAMPTOSAR was administered in repeated 6-week cycles consisting of a 90-minute intravenous infusion once weekly for 4 weeks, followed by a 2-week rest period. Starting doses of CAMPTOSAR in these trials were 100, 125, or 150 mg/m^2, but the 150-mg/m^2 dose was poorly tolerated (due to high rates of grade 4 late diarrhea and febrile neutropenia). Study 3 enrolled 48 patients and was conducted by a single investigator at several regional hospitals. Study 4 was a multicenter study conducted by the North Central Cancer Treatment Group. All 90 patients enrolled in Study 4 received a starting dose of 125 mg/m^2. Study 5 was a multicenter study that enrolled 166 patients from 30 institutions. The initial dose in Study 5 was 125 mg/m^2 but was reduced to 100 mg/m^2 because the toxicity seen at the 125-mg/m^2 dose was perceived to be greater than that seen in previous studies. All patients in these studies had metastatic colorectal cancer, and the majority had disease that recurred or progressed following a 5-FU-based regimen administered for metastatic disease. The results of the individual studies are shown in Table 11.

Table 11. Weekly Dosage Schedule: Study Results
 | Study
 | 3 | 4 | 5
Number of Patients | 48 | 90 | 64 | 102
Starting Dose (mg/m^2/week × 4) | 125 [Nine patients received 150 mg/m^2 as a starting dose; two (22.2%) responded to CAMPTOSAR.] | 125 | 125 | 100
Demographics and Treatment Administration
Female/Male (%) | 46/54 | 36/64 | 50/50 | 51/49
Median Age in years (range) | 63 (29–78) | 63 (32–81) | 61 (42–84) | 64 (25–84)
Ethnic Origin (%)
White | 79 | 96 | 81 | 91
African American | 12 | 4 | 11 | 5
Hispanic | 8 | 0 | 8 | 2
Oriental/Asian | 0 | 0 | 0 | 2
Performance Status (%)
0 | 60 | 38 | 59 | 44
1 | 38 | 48 | 33 | 51
2 | 2 | 14 | 8 | 5
Primary Tumor (%)
Colon | 100 | 71 | 89 | 87
Rectum | 0 | 29 | 11 | 8
Unknown | 0 | 0 | 0 | 5
Prior 5-FU Therapy (%)
For Metastatic Disease | 81 | 66 | 73 | 68
≤ 6 months after Adjuvant | 15 | 7 | 27 | 28
> 6 months after Adjuvant | 2 | 16 | 0 | 2
Classification Unknown | 2 | 12 | 0 | 3
Prior Pelvic/Abdominal Irradiation (%)
Yes | 3 | 29 | 0 | 0
Other | 0 | 9 | 2 | 4
None | 97 | 62 | 98 | 96
Duration of Treatment with CAMPTOSAR (median, months) | 5 | 4 | 4 | 3
Relative Dose Intensity [Relative dose intensity for CAMPTOSAR based on planned dose intensity of 100, 83.3, and 66.7 mg/m^2/wk corresponding with 150, 125, and 100 mg/m^2 starting doses, respectively.] (median %) | 74 | 67 | 73 | 81
Efficacy
Confirmed Objective Response Rate (%) [Confirmed ≥ 4 to 6 weeks after first evidence of objective response.] (95% CI) | 21 (9.3 – 32.3) | 13 (6.3 – 20.4) | 14 (5.5 – 22.6) | 9 (3.3 – 14.3)
Time to Response (median, months) | 2.6 | 1.5 | 2.8 | 2.8
Response Duration (median, months) | 6.4 | 5.9 | 5.6 | 6.4
Survival (median, months) | 10.4 | 8.1 | 10.7 | 9.3
1-Year Survival (%) | 46 | 31 | 45 | 43

In the intent-to-treat analysis of the pooled data across all three studies, 193 of the 304 patients began therapy at the recommended starting dose of 125 mg/m^2. Among these 193 patients, 2 complete and 27 partial responses were observed, for an overall response rate of 15.0% (95% Confidence Interval [CI], 10.0% to 20.1%) at this starting dose. A considerably lower response rate was seen with a starting dose of 100 mg/m^2. The majority of responses were observed within the first two cycles of therapy, but responses did occur in later cycles of treatment (one response was observed after the eighth cycle). The median response duration for patients beginning therapy at 125 mg/m^2 was 5.8 months (range, 2.6 to 15.1 months). Of the 304 patients treated in the three studies, response rates to CAMPTOSAR were similar in males and females and among patients older and younger than 65 years. Rates were also similar in patients with cancer of the colon or cancer of the rectum and in patients with single and multiple metastatic sites. The response rate was 18.5% in patients with a performance status of 0 and 8.2% in patients with a performance status of 1 or 2. Patients with a performance status of 3 or 4 have not been studied. Over half of the patients responding to CAMPTOSAR had not responded to prior 5-FU. Patients who had received previous irradiation to the pelvis responded to CAMPTOSAR at approximately the same rate as those who had not previously received irradiation.

Once-Every-3-Week Dosage Schedule

Single Arm Study: Study 6

Data from an open-label, single-agent, single-arm, multicenter, clinical study involving a total of 132 patients support a once every-3-week dosage schedule of irinotecan in the treatment of patients with metastatic cancer of the colon or rectum that recurred or progressed following treatment with 5-FU. Patients received a starting dose of 350 mg/m^2 given by 30-minute intravenous infusion once every 3 weeks. Among the 132 previously treated patients in this trial, the intent-to-treat response rate was 12.1% (95% CI, 7.0% to 18.1%).

Randomized Studies: Studies 7 and 8

Two multicenter, randomized, clinical studies further support the use of irinotecan given by the once-every-3-week dosage schedule in patients with metastatic colorectal cancer whose disease has recurred or progressed following prior 5-FU therapy. In Study 7, second-line irinotecan therapy plus best supportive care was compared with best supportive care alone. In Study 8, second-line irinotecan therapy was compared with infusional 5-FU-based therapy. In both studies, irinotecan was administered intravenously at a starting dose of 350 mg/m^2 over 90 minutes once every 3 weeks. The starting dose was 300 mg/m^2 for patients who were 70 years and older or who had a performance status of 2. The highest total dose permitted was 700 mg. Dose reductions and/or administration delays were permitted in the event of severe hematologic and/or nonhematologic toxicities while on treatment. Best supportive care was provided to patients in both arms of Study 7 and included antibiotics, analgesics, corticosteroids, transfusions, psychotherapy, or any other symptomatic therapy as clinically indicated. In both studies, concomitant medications such as antiemetics, atropine, and loperamide were given to patients for prophylaxis and/or management of symptoms from treatment. If late diarrhea persisted for greater than 24 hours despite loperamide, a 7-day course of fluoroquinolone antibiotic prophylaxis was given. Patients in the control arm of the Study 8 received one of the following 5-FU regimens: (1) LV, 200 mg/m^2 IV over 2 hours; followed by 5-FU, 400 mg/m^2 IV bolus; followed by 5-FU, 600 mg/m^2 continuous IV infusion over 22 hours on days 1 and 2 every 2 weeks; (2) 5-FU, 250 to 300 mg/m^2/day protracted continuous IV infusion until toxicity; (3) 5-FU, 2.6 to 3 g/m^2 IV over 24 hours every week for 6 weeks with or without LV, 20 to 500 mg/m^2/day every week IV for 6 weeks with 2-week rest between cycles. Patients were to be followed every 3 to 6 weeks for 1 year.

A total of 535 patients were randomized in the two studies at 94 centers. The primary endpoint in both studies was survival. The studies demonstrated a significant overall survival advantage for irinotecan compared with best supportive care (p=0.0001) and infusional 5-FU-based therapy (p=0.035) as shown in Figures 3 and 4. In Study 7, median survival for patients treated with irinotecan was 9.2 months compared with 6.5 months for patients receiving best supportive care. In Study 8, median survival for patients treated with irinotecan was 10.8 months compared with 8.5 months for patients receiving infusional 5-FU-based therapy. Multiple regression analyses determined that patients' baseline characteristics also had a significant effect on survival. When adjusted for performance status and other baseline prognostic factors, survival among patients treated with irinotecan remained significantly longer than in the control populations (p=0.001 for Study 7 and p=0.017 for Study 8). Measurements of pain, performance status, and weight loss were collected prospectively in the two studies; however, the plan for the analysis of these data was defined retrospectively. When comparing irinotecan with best supportive care in Study 7, this analysis showed a statistically significant advantage for irinotecan, with longer time to development of pain (6.9 months versus 2.0 months), time to performance status deterioration (5.7 months versus 3.3 months), and time to > 5% weight loss (6.4 months versus 4.2 months). Additionally, 33.3% (33/99) of patients with a baseline performance status of 1 or 2 showed an improvement in performance status when treated with irinotecan versus 11.3% (7/62) of patients receiving best supportive care (p=0.002). Because of the inclusion of patients with non-measurable disease, intent-to-treat response rates could not be assessed.

Figure 3. Survival Second-Line Irinotecan vs Best Supportive Care (BSC)
Study 7

Figure 4. Survival Second-Line Irinotecan vs Infusion 5-FU
Study 8

Table 12. Once-Every-3-Week Dosage Schedule: Study Results
 | Study 7 |  | Study 8
 | Irinotecan | BSC [BSC = best supportive care] | Irinotecan | 5-FU
Number of patients | 189 | 90 | 127 | 129
Demographics and treatment administration
Female/Male (%) | 32/68 | 42/58 | 43/57 | 35/65
Median age in years (range) | 59 (22–75) | 62 (34–75) | 58 (30–75) | 58 (25–75)
Performance status (%)
0 | 47 | 31 | 58 | 54
1 | 39 | 46 | 35 | 43
2 | 14 | 23 | 8 | 3
Primary tumor (%)
Colon | 55 | 52 | 57 | 62
Rectum | 45 | 48 | 43 | 38
Prior 5-FU therapy (%)
For metastatic disease | 70 | 63 | 58 | 68
As adjuvant treatment | 30 | 37 | 42 | 32
Prior irradiation (%) | 26 | 27 | 18 | 20
Duration of study treatment (median, months) (Log-rank test) | 4.1 | -- | 4.2 (p=0.02) | 2.8
Relative dose intensity (median %) [Relative dose intensity for irinotecan based on planned dose intensity of 116.7 and 100 mg/m^2/wk corresponding with 350 and 300 mg/m^2 starting doses, respectively.] | 94 | -- | 95 | 81–99
Survival
Survival (median, months) | 9.2 | 6.5 | 10.8 | 8.5
(Log-rank test) | (p=0.0001) |  | (p=0.035)

In the two randomized studies, the EORTC QLQ-C30 instrument was utilized. At the start of each cycle of therapy, patients completed a questionnaire consisting of 30 questions, such as "Did pain interfere with daily activities?" (1 = Not at All, to 4 = Very Much) and "Do you have any trouble taking a long walk?" (Yes or No). The answers from the 30 questions were converted into 15 subscales, that were scored from 0 to 100, and the global health status subscale that was derived from two questions about the patient's sense of general well being in the past week. The results as summarized in Table 13 are based on patients' worst post-baseline scores. In Study 7, a multivariate analysis and univariate analyses of the individual subscales were performed and corrected for multivariate testing. Patients receiving irinotecan reported significantly better results for the global health status, on two of five functional subscales, and on four of nine symptom subscales. As expected, patients receiving irinotecan noted significantly more diarrhea than those receiving best supportive care. In Study 8, the multivariate analysis on all 15 subscales did not indicate a statistically significant difference between irinotecan and infusional 5-FU.

Table 13. EORTC QLQ-C30: Mean Worst Post-Baseline Score [For the five functional subscales and global health status subscale, higher scores imply better functioning, whereas, on the nine symptom subscales, higher scores imply more severe symptoms. The subscale scores of each patient were collected at each visit until the patient dropped out of the study.]
QLQ-C30 Subscale | Study 7 |  |  | Study 8
QLQ-C30 Subscale | Irinotecan | BSC | p-value | Irinotecan | 5-FU | p-value
Global health status | 47 | 37 | 0.03 | 53 | 52 | 0.9
Functional scales
Cognitive | 77 | 68 | 0.07 | 79 | 83 | 0.9
Emotional | 68 | 64 | 0.4 | 64 | 68 | 0.9
Social | 58 | 47 | 0.06 | 65 | 67 | 0.9
Physical | 60 | 40 | 0.0003 | 66 | 66 | 0.9
Role | 53 | 35 | 0.02 | 54 | 57 | 0.9
Symptom Scales
Fatigue | 51 | 63 | 0.03 | 47 | 46 | 0.9
Appetite loss | 37 | 57 | 0.0007 | 35 | 38 | 0.9
Pain assessment | 41 | 56 | 0.009 | 38 | 34 | 0.9
Insomnia | 39 | 47 | 0.3 | 39 | 33 | 0.9
Constipation | 28 | 41 | 0.03 | 25 | 19 | 0.9
Dyspnea | 31 | 40 | 0.2 | 25 | 24 | 0.9
Nausea/Vomiting | 27 | 29 | 0.5 | 25 | 16 | 0.09
Financial impact | 22 | 26 | 0.5 | 24 | 15 | 0.3
Diarrhea | 32 | 19 | 0.01 | 32 | 22 | 0.2

15 REFERENCES

1. "OSHA Hazardous Drugs." OSHA. http://www.osha.gov/SLTC/hazardousdrugs/index.html

16 HOW SUPPLIED/STORAGE AND HANDLING

CAMPTOSAR (irinotecan hydrochloride) Injection is available as a sterile, pale yellow, clear, aqueous solution in an amber colored polypropylene CYTOSAFE® vial packaged as follows:

Unit of Sale | Total Strength/Total Volume; (Concentration)
NDC 0009-7529-04; Carton of 1 single-dose vial | 40 mg/2 mL; (20 mg/mL)
NDC 0009-7529-03; Carton of 1 single-dose vial | 100 mg/5 mL; (20 mg/mL)
NDC 0009-7529-05; Carton of 1 single-dose vial | 300 mg/15 mL; (20 mg/mL)

CAMPTOSAR (irinotecan hydrochloride) Injection is available as an amber colored ONCO‑TAIN® glass vial packaged as follows:

Unit of Sale | Total Strength/Total Volume (Concentration)
NDC 0009-7529-10; Carton of 1 single-dose vial | 40 mg/2 mL; (20 mg/mL)
NDC 0009-0112-05; Carton of 1 single-dose vial | 100 mg/5 mL; (20 mg/mL)
NDC 0009-0082-02; Carton of 1 single-dose vial | 300 mg/15 mL; (20 mg/mL)

ONCO-TAIN® is the vial external protection system.

Store at controlled room temperature 15°C to 30°C (59° to 86°F). Protect from freezing. Protect from light. Keep the vial in the carton until the time of use.

STORAGE AND HANDLING

Inspect the vial for damage and visible signs of leaks before removing from the carton. If damaged, incinerate the unopened package.

CAMPTOSAR is a hazardous drug. Follow special handling and disposal procedures.1

17 PATIENT COUNSELING INFORMATION

- Patients and caregivers should be informed of gastrointestinal complications, such as nausea, vomiting, abdominal cramping, and diarrhea. Patients should have loperamide readily available to begin treatment for late diarrhea (generally occurring more than 24 hours after administration of CAMPTOSAR). Begin loperamide at the first episode of poorly formed or loose stools or the earliest onset of bowel movements more frequent than normal. One dosage regimen for loperamide is 4 mg at the first onset of late diarrhea and then 2 mg every 2 hours until the patient is diarrhea-free for at least 12 hours. Loperamide is not recommended to be used for more than 48 consecutive hours at these doses, because of the risk of paralytic ileus. During the night, the patient may take 4 mg of loperamide every 4 hours. Patients should contact their physician if any of the following occur: diarrhea for the first time during treatment; black or bloody stools; symptoms of dehydration such as lightheadedness, dizziness, or faintness; inability to take fluids by mouth due to nausea or vomiting; or inability to get diarrhea under control within 24 hours.
- Patients should be warned about the potential for dizziness or visual disturbances which may occur within 24 hours following the administration of CAMPTOSAR.
- Explain the significance of routine blood cell counts. Instruct patients to monitor their temperature frequently and immediately report any occurrence of fever or infection.
- Embryo-Fetal Toxicity [see Warnings and Precautions (5.9), Use in Specific Populations (8.1, 8.3), Clinical Pharmacology (12.1) and Nonclinical Toxicology (13.1)]
  - Advise pregnant women and females of reproductive potential of the potential risk to a fetus and to inform their healthcare provider of a known or suspected pregnancy.
  - Advise females of reproductive potential to use effective contraception during treatment with CAMPTOSAR and for 6 months after the final dose.
  - Advise male patients with female partners of reproductive potential to use condoms during treatment and for 3 months after the final dose of CAMPTOSAR.
- Lactation
  - Advise women not to breastfeed during treatment with CAMPTOSAR and for at least 7 days after the final dose [see Use in Specific Populations (8.2)].
- Infertility
  - Advise females and males of reproductive potential that CAMPTOSAR may impair fertility [see Use in Specific Populations (8.3)].
- Patients should be alerted to the possibility of alopecia.
- Contains sorbitol.

This product's labeling may have been updated. For the most recent prescribing information, please visit www.pfizer.com.

For medical information about CAMPTOSAR, please visit www.pfizermedinfo.com or call 1‑800-438-1985.

LAB-0134-25.0

PACKAGE LABEL

PRINCIPAL DISPLAY PANEL - 100 mg/5 mL Vial Label

NDC 0009-7529-03
Single-dose: Discard unused portion

Camptosar®
irinotecan HCl injection

100 mg/5 mL
(20 mg/mL)

For Intravenous Use Only
Cytosafe® Vial
Caution: Cytotoxic Agent

PACKAGE LABEL

PRINCIPAL DISPLAY PANEL - 100 mg/5 mL Vial Carton

NDC 0009-7529-03

Single-dose: Discard unused portion
Camptosar®
irinotecan hydrochloride
injection

100 mg/5 mL
(20 mg/mL)

For Intravenous Use Only

Cytosafe® Vial
Caution: Cytotoxic Agent

Pfizer Injectables

Rx only

PRINCIPAL DISPLAY PANEL - 40 mg/2 mL Vial Label

NDC 0009-7529-10
Camptosar®
irinotecan HCL injection
40mg/ 2mL
(20 mg/mL) Warning: Hazardous Drug
For Intravenous Use Only.
Single-dose vial. Discard unused portion.

PRINCIPAL DISPLAY PANEL - 40 mg/2 mL Vial Carton

NDC 0009-7529-10

One 2 mL Single-dose vial
Discard unused portion
Camptosar®
irinotecan hydrochloride
injection

40 mg/2 mL
(20 mg/mL)

For Intravenous Use Only

MUST DILUTE BEFORE USE

Pfizer Hospital

Rx only

PRINCIPAL DISPLAY PANEL - 100 mg/5 mL Vial Label (0112)

NDC 0009-0112-05
Camptosar®
irinotecan HCL injection
100 mg/5 mL
(20 mg/mL)
For Intravenous Use Only
Single-dose vial. Discard Unused portion
Warning: Hazardous Drug

PRINCIPAL DISPLAY PANEL - 100 mg/5 mL Vial Carton (0112)

NDC 0009-0112-05

One 5 mL Single-dose vial
Discard unused portion
Camptosar®
irinotecan hydrochloride
injection

100 mg/5 mL
(20 mg/mL)
For Intravenous Use Only
MUST DILUTE BEFORE USE
Pfizer Hospital

Rx only

PRINCIPAL DISPLAY PANEL - 300 mg/15 mL Vial Label

NDC 0009-0082-02
Camptosar®
irinotecan HCL injection
300 mg/ 15 mL
(20 mg/mL)
For Intravenous Use Only
Single-dose vial. Discard unused portion
Warning: Hazardous Drug
Rx Only

PRINCIPAL DISPLAY PANEL - 300 mg/15 mL Vial Carton

NDC 0009-0082-02
One 15 mL Single-dose vial.
Discard unused portion
Camptosar
irinotecan hydrochloride
injection
300 mg/15 mL
(20mg/mL)

For Intravenous Use Only
MUST DILUTE BEFORE USE
Pfizer Hospital
Rx only